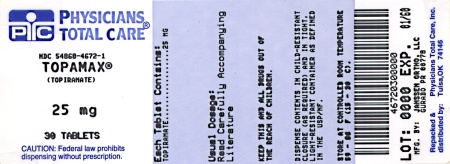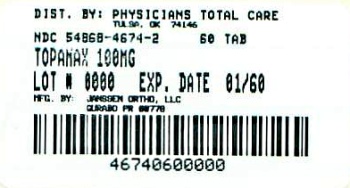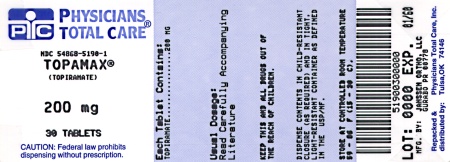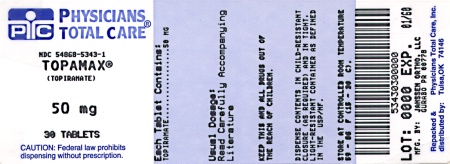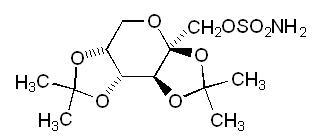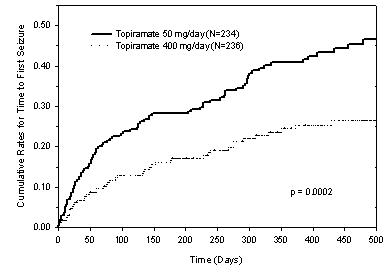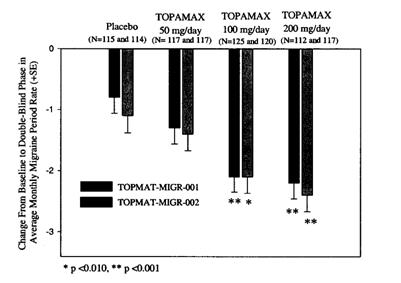 DRUG LABEL: Topamax
NDC: 54868-4672 | Form: TABLET, COATED
Manufacturer: Physicians Total Care, Inc.
Category: prescription | Type: HUMAN PRESCRIPTION DRUG LABEL
Date: 20120214

ACTIVE INGREDIENTS: topiramate 25 mg/1 1
INACTIVE INGREDIENTS: lactose monohydrate; cellulose, microcrystalline; sodium starch glycolate type A potato; magnesium stearate; water; carnauba wax; hypromelloses; titanium dioxide; polyethylene glycols; polysorbate 80

HIGHLIGHTS OF PRESCRIBING INFORMATION

These highlights do not include all the information needed to use TOPAMAX® safely and effectively. See full prescribing information for TOPAMAX®
TOPAMAX (topiramate) TABLETS for oral use
TOPAMAX (topiramate capsules) SPRINKLE CAPSULES for oral use
Initial U.S. Approval – 1996

RECENT MAJOR CHANGES

• Indications and Usage (1.1) | 07/2011
• Dosage and Administration (2.1) | 07/2011
• Metabolic Acidosis (5.3) | 07/2011
• Hypothermia with Concomitant Valproic Acid (VPA) Use (5.11) | 07/2011

1 INDICATIONS AND USAGE

TOPAMAX® is an antiepileptic (AED) agent indicated for:

- Monotherapy epilepsy: Initial monotherapy in patients ≥ 2 years of age with partial onset or primary generalized tonic-clonic seizures (1.1)
- Adjunctive therapy epilepsy: Adjunctive therapy for adults and pediatric patients (2 to 16 years of age) with partial onset seizures or primary generalized tonic-clonic seizures, and in patients ≥2 years of age with seizures associated with Lennox-Gastaut syndrome (LGS) (1.2)
- Migraine: Treatment for adults for prophylaxis of migraine headache (1.3)

2 DOSAGE AND ADMINISTRATION

See DOSAGE AND ADMINISTRATION, Epilepsy: Monotherapy and Adjunctive Therapy Use for additional details (2.1)

 | Initial Dose | Titration | Recommended Dose
Epilepsy monotherapy: children 2 to <10 years (2.1) | 25 mg/day administered nightly for the first week | The dosage should be titrated over 5–7 weeks | Daily doses in two divided doses based on weight (Table 2)
Epilepsy monotherapy: adults and pediatric patients ≥10 years (2.1) | 50 mg/day in two divided doses | The dosage should be increased weekly by increments of 50 mg for the first 4 weeks then 100 mg for weeks 5 to 6. | 400 mg/day in two divided doses
Epilepsy adjunctive therapy: adults with partial onset seizures or LGS (2.1) | 25 to 50 mg/day | The dosage should be increased weekly to an effective dose by increments of 25 to 50 mg. | 200–400 mg/day in two divided doses
Epilepsy adjunctive therapy: adults with primary generalized tonic-clonic seizures (2.1) | 25 to 50 mg/day | The dosage should be increased weekly to an effective dose by increments of 25 to 50 mg. | 400 mg/day in two divided doses
Epilepsy adjunctive therapy: pediatric patients with partial onset seizures, primary generalized tonic-clonic seizures or LGS (2.1) | 25 mg/day (or less, based on a range of 1 to 3 mg/kg/day) nightly for the first week | The dosage should be increased at 1- or 2-week intervals by increments of 1 to 3 mg/kg/day (administered in two divided doses). Dose titration should be guided by clinical outcome. | 5 to 9 mg/kg/day in two divided doses
Migraine (2.2) | 25 mg/day administered nightly for the first week | The dosage should be increased weekly by increments of 25 mg. Dose and titration should be guided by clinical outcome. | 100 mg/day administered in two divided doses

3 DOSAGE FORMS AND STRENGTHS

- Tablets: 25 mg, 50 mg, 100 mg, and 200 mg (3)
- Sprinkle Capsules: 15 mg and 25 mg (3)

4 CONTRAINDICATIONS

None.

5 WARNINGS AND PRECAUTIONS

- Acute myopia and secondary angle closure glaucoma: Untreated elevated intraocular pressure can lead to permanent visual loss. The primary treatment to reverse symptoms is discontinuation of TOPAMAX® as rapidly as possible (5.1)
- Oligohidrosis and hyperthermia: Monitor decreased sweating and increased body temperature, especially in pediatric patients (5.2)
- Metabolic acidosis: Baseline and periodic measurement of serum bicarbonate is recommended. Consider dose reduction or discontinuation of TOPAMAX® if clinically appropriate (5.3)
- Suicidal behavior and ideation: Antiepileptic drugs increase the risk of suicidal behavior or ideation (5.4)
- Cognitive/neuropsychiatric: TOPAMAX® may cause cognitive dysfunction. Patients should use caution when operating machinery including automobiles. Depression and mood problems may occur in epilepsy and migraine populations (5.5)
- Fetal Toxicity: TOPAMAX® use during pregnancy can cause cleft lip and/or palate (5.6)
- Withdrawal of AEDs: Withdrawal of TOPAMAX® should be done gradually (5.7)
- Hyperammonemia and encephalopathy associated with or without concomitant valproic acid use: Patients with inborn errors of metabolism or reduced mitochondrial activity may have an increased risk of hyper-ammonemia. Measure ammonia if encephalopathic symptoms occur (5.9)
- Kidney stones: Use with other carbonic anhydrase inhibitors, other drugs causing metabolic acidosis, or in patients on a ketogenic diet should be avoided (5.10)
- Hypothermia has been reported with and without hyperammonemia during topiramate treatment with concomitant valproic acid use (5.11)

6 ADVERSE REACTIONS

The most common (≥5% more frequent than placebo or low-dose TOPAMAX® in monotherapy) adverse reactions in controlled, epilepsy clinical trials were paresthesia, anorexia, weight decrease, fatigue, dizziness, somnolence, nervousness, psychomotor slowing, difficulty with memory, difficulty with concentration/attention, cognitive problems, confusion, mood problems, fever, infection, and flushing. The most common (≥5% more frequent than placebo) adverse reactions in controlled, migraine clinical trials were paresthesia and taste perversion (6) .

To report SUSPECTED ADVERSE REACTIONS, contact Janssen Pharmaceuticals, Inc. at 1-800-JANSSEN (1-800-526-7736) or FDA at 1-800-FDA-1088 or WWW.FDA.GOV/MEDWATCH.

7 DRUG INTERACTIONS

Summary of antiepileptic drug (AED) interactions with TOPAMAX® (7.1)

AED Co-administered | AED Concentration | Topiramate Concentration
Phenytoin | NC or 25% increase [= Plasma concentration increased 25% in some patients, generally those on a twice a day dosing regimen of phenytoin.] | 48% decrease
Carbamazepine (CBZ) | NC | 40% decrease
CBZ epoxide [= Is not administered but is an active metabolite of carbamazepine.] | NC | NE
Valproic acid | 11% decrease | 14% decrease
Phenobarbital | NC | NE
Primidone | NC | NE
Lamotrigine | NC at TPM doses up to 400 mg/day | 13% decrease
NC = Less than 10% change in plasma concentration.
NE = Not Evaluated

- Oral contraceptives: Decreased contraceptive efficacy and increased breakthrough bleeding should be considered, especially at doses greater than 200 mg/day (7.3)
- Metformin is contraindicated with metabolic acidosis, an effect of TOPAMAX® (7.4)
- Lithium levels should be monitored when co-administered with high-dose TOPAMAX® (7.5)
- Other carbonic anhydrase inhibitors: Monitor the patient for the appearance or worsening of metabolic acidosis (7.6)

8 USE IN SPECIFIC POPULATIONS

- Renal impairment: In renally impaired patients (creatinine clearance less than 70 mL/min/1.73 m^2), one-half of the adult dose is recommended (2.4)
- Patients undergoing hemodialysis: Topiramate is cleared by hemodialysis. Dosage adjustment is necessary to avoid rapid drops in topiramate plasma concentration during hemodialysis (2.6)
- Pregnancy: Increased risk of cleft lip and/or palate. Pregnancy registry available (8.1)
- Nursing mothers: Caution should be exercised when administered to a nursing mother (8.3)
- Geriatric use: Dosage adjustment may be necessary for elderly with impaired renal function (8.5)

FULL PRESCRIBING INFORMATION

1 INDICATIONS AND USAGE

1.1 Monotherapy Epilepsy

TOPAMAX® (topiramate) Tablets and TOPAMAX® (topiramate capsules) Sprinkle Capsules are indicated as initial monotherapy in patients 2 years of age and older with partial onset or primary generalized tonic-clonic seizures. Safety and effectiveness in patients who were converted to monotherapy from a previous regimen of other anticonvulsant drugs have not been established in controlled trials [see Clinical Studies (14.1)].

1.2 Adjunctive Therapy Epilepsy

TOPAMAX® Tablets and TOPAMAX® Sprinkle Capsules are indicated as adjunctive therapy for adults and pediatric patients ages 2 to 16 years with partial onset seizures or primary generalized tonic-clonic seizures, and in patients 2 years of age and older with seizures associated with Lennox-Gastaut syndrome [see Clinical Studies (14.2)].

1.3 Migraine

TOPAMAX® Tablets and TOPAMAX® Sprinkle Capsules are indicated for adults for the prophylaxis of migraine headache [see Clinical Studies (14.3)]. The usefulness of TOPAMAX® in the acute treatment of migraine headache has not been studied.

2 DOSAGE AND ADMINISTRATION

2.1 Epilepsy

It is not necessary to monitor topiramate plasma concentrations to optimize TOPAMAX® (topiramate) therapy.

On occasion, the addition of TOPAMAX® to phenytoin may require an adjustment of the dose of phenytoin to achieve optimal clinical outcome. Addition or withdrawal of phenytoin and/or carbamazepine during adjunctive therapy with TOPAMAX® may require adjustment of the dose of TOPAMAX®.

Because of the bitter taste, tablets should not be broken.

TOPAMAX® can be taken without regard to meals.

Monotherapy Use

Adults and Pediatric Patients 10 Years and Older

The recommended dose for TOPAMAX® monotherapy in adults and pediatric patients 10 years of age and older is 400 mg/day in two divided doses. Approximately 58% of patients randomized to 400 mg/day achieved this maximal dose in the monotherapy controlled trial; the mean dose achieved in the trial was 275 mg/day. The dose should be achieved by titration according to the following schedule (Table 1):

Table 1: Monotherapy Titration Schedule for Adults and Pediatric Patients 10 years and older
 | Morning Dose | Evening Dose
Week 1 | 25 mg | 25 mg
Week 2 | 50 mg | 50 mg
Week 3 | 75 mg | 75 mg
Week 4 | 100 mg | 100 mg
Week 5 | 150 mg | 150 mg
Week 6 | 200 mg | 200 mg

Children Ages 2 to <10 Years

Dosing of topiramate as initial monotherapy in children 2 to < 10 years of age with partial onset or primary generalized tonic-clonic seizures was based on a pharmacometric bridging approach [see Clinical Studies (14.1)].

Dosing in patients 2 to <10 years is based on weight. During the titration period, the initial dose of TOPAMAX® should be 25 mg/day administered nightly for the first week. Based upon tolerability, the dosage can be increased to 50 mg/day (25 mg twice daily) in the second week. Dosage can be increased by 25–50 mg/day each subsequent week as tolerated. Titration to the minimum maintenance dose should be attempted over 5–7 weeks of the total titration period. Based upon tolerability and seizure control, additional titration to a higher dose (up to the maximum maintenance dose) can be attempted at 25–50 mg/day weekly increments. The total daily dose should not exceed the maximum maintenance dose for each range of body weight (Table 2).

Table 2: Monotherapy Target Total Daily Maintenance Dosing for Patients 2 to <10 Years
Weight (kg) | Total Daily Dose (mg/day) [Administered in two equally divided doses] Minimum Maintenance Dose | Total Daily Dose (mg/day) Maximum Maintenance Dose
Up to 11 | 150 | 250
12 – 22 | 200 | 300
23 – 31 | 200 | 350
32 – 38 | 250 | 350
Greater than 38 | 250 | 400

Adjunctive Therapy Use

Adults 17 Years of Age and Over - Partial Onset Seizures, Primary Generalized Tonic-Clonic Seizures, or Lennox-Gastaut Syndrome

The recommended total daily dose of TOPAMAX® as adjunctive therapy in adults with partial onset seizures is 200 to 400 mg/day in two divided doses, and 400 mg/day in two divided doses as adjunctive treatment in adults with primary generalized tonic-clonic seizures. It is recommended that therapy be initiated at 25 to 50 mg/day followed by titration to an effective dose in increments of 25 to 50 mg/day every week. Titrating in increments of 25 mg/day every week may delay the time to reach an effective dose. Doses above 400 mg/day (600, 800 or 1,000 mg/day) have not been shown to improve responses in dose-response studies in adults with partial onset seizures. Daily doses above 1,600 mg have not been studied.

In the study of primary generalized tonic-clonic seizures, the initial titration rate was slower than in previous studies; the assigned dose was reached at the end of 8 weeks [see Clinical Studies (14.1)].

Pediatric Patients Ages 2 – 16 Years – Partial Onset Seizures, Primary Generalized Tonic-Clonic Seizures, or Lennox-Gastaut Syndrome

The recommended total daily dose of TOPAMAX® as adjunctive therapy for pediatric patients with partial onset seizures, primary generalized tonic-clonic seizures, or seizures associated with Lennox-Gastaut syndrome is approximately 5 to 9 mg/kg/day in two divided doses. Titration should begin at 25 mg/day (or less, based on a range of 1 to 3 mg/kg/day) nightly for the first week. The dosage should then be increased at 1- or 2-week intervals by increments of 1 to 3 mg/kg/day (administered in two divided doses), to achieve optimal clinical response. Dose titration should be guided by clinical outcome.

In the study of primary generalized tonic-clonic seizures, the initial titration rate was slower than in previous studies; the assigned dose of 6 mg/kg/day was reached at the end of 8 weeks [see Clinical Studies (14.1)].

2.2 Migraine

The recommended total daily dose of TOPAMAX® as treatment for adults for prophylaxis of migraine headache is 100 mg/day administered in two divided doses (Table 3). The recommended titration rate for topiramate for migraine prophylaxis to 100 mg/day is:

Table 3: Migraine Prophylaxis Titration Schedule for Adults
 | Morning Dose | Evening Dose
Week 1 | None | 25 mg
Week 2 | 25 mg | 25 mg
Week 3 | 25 mg | 50 mg
Week 4 | 50 mg | 50 mg

Dose and titration rate should be guided by clinical outcome. If required, longer intervals between dose adjustments can be used.

TOPAMAX® can be taken without regard to meals.

2.3 Administration of TOPAMAX® Sprinkle Capsules

TOPAMAX® (topiramate capsules) Sprinkle Capsules may be swallowed whole or may be administered by carefully opening the capsule and sprinkling the entire contents on a small amount (teaspoon) of soft food. This drug/food mixture should be swallowed immediately and not chewed. It should not be stored for future use.

2.4 Patients with Renal Impairment

In renally impaired subjects (creatinine clearance less than 70 mL/min/1.73 m^2), one-half of the usual adult dose is recommended. Such patients will require a longer time to reach steady-state at each dose.

2.5 Geriatric Patients (Ages 65 Years and Over)

Dosage adjustment may be indicated in the elderly patient when impaired renal function (creatinine clearance rate <70 mL/min/1.73 m^2) is evident [see Clinical Pharmacology (12.3)].

2.6 Patients Undergoing Hemodialysis

Topiramate is cleared by hemodialysis at a rate that is 4 to 6 times greater than a normal individual. Accordingly, a prolonged period of dialysis may cause topiramate concentration to fall below that required to maintain an anti-seizure effect. To avoid rapid drops in topiramate plasma concentration during hemodialysis, a supplemental dose of topiramate may be required. The actual adjustment should take into account 1) the duration of dialysis period, 2) the clearance rate of the dialysis system being used, and 3) the effective renal clearance of topiramate in the patient being dialyzed.

2.7 Patients with Hepatic Disease

In hepatically impaired patients, topiramate plasma concentrations may be increased. The mechanism is not well understood.

3 DOSAGE FORMS AND STRENGTHS

TOPAMAX® (topiramate) Tablets are available as debossed, coated, round tablets in the following strengths and colors:

25 mg cream (debossed "OMN" on one side; "25" on the other)

50 mg light-yellow (debossed "OMN" on one side; "50" on the other)

100 mg yellow (debossed "OMN" on one side; "100" on the other)

200 mg salmon (debossed "OMN" on one side; "200" on the other)

TOPAMAX® (topiramate capsules) Sprinkle Capsules contain small, white to off-white spheres. The gelatin capsules are white and clear.

They are marked as follows:

15 mg capsule with "TOP" and "15 mg" on the side

25 mg capsule with "TOP" and "25 mg" on the side

4 CONTRAINDICATIONS

None.

5 WARNINGS AND PRECAUTIONS

5.1 Acute Myopia and Secondary Angle Closure Glaucoma

A syndrome consisting of acute myopia associated with secondary angle closure glaucoma has been reported in patients receiving TOPAMAX® (topiramate). Symptoms include acute onset of decreased visual acuity and/or ocular pain. Ophthalmologic findings can include myopia, anterior chamber shallowing, ocular hyperemia (redness), and increased intraocular pressure. Mydriasis may or may not be present. This syndrome may be associated with supraciliary effusion resulting in anterior displacement of the lens and iris, with secondary angle closure glaucoma. Symptoms typically occur within 1 month of initiating TOPAMAX® therapy. In contrast to primary narrow angle glaucoma, which is rare under 40 years of age, secondary angle closure glaucoma associated with topiramate has been reported in pediatric patients as well as adults. The primary treatment to reverse symptoms is discontinuation of TOPAMAX® as rapidly as possible, according to the judgment of the treating physician. Other measures, in conjunction with discontinuation of TOPAMAX®, may be helpful.

Elevated intraocular pressure of any etiology, if left untreated, can lead to serious sequelae including permanent vision loss.

5.2 Oligohidrosis and Hyperthermia

Oligohidrosis (decreased sweating), infrequently resulting in hospitalization, has been reported in association with TOPAMAX® use. Decreased sweating and an elevation in body temperature above normal characterized these cases. Some of the cases were reported after exposure to elevated environmental temperatures.

The majority of the reports have been in pediatric patients. Patients, especially pediatric patients, treated with TOPAMAX® should be monitored closely for evidence of decreased sweating and increased body temperature, especially in hot weather. Caution should be used when TOPAMAX® is prescribed with other drugs that predispose patients to heat-related disorders; these drugs include, but are not limited to, other carbonic anhydrase inhibitors and drugs with anticholinergic activity.

5.3 Metabolic Acidosis

Hyperchloremic, non-anion gap, metabolic acidosis (i.e., decreased serum bicarbonate below the normal reference range in the absence of chronic respiratory alkalosis) is associated with TOPAMAX® treatment. This metabolic acidosis is caused by renal bicarbonate loss due to the inhibitory effect of topiramate on carbonic anhydrase. Such electrolyte imbalance has been observed with the use of topiramate in placebo-controlled clinical trials and in the post-marketing period. Generally, topiramate-induced metabolic acidosis occurs early in treatment although cases can occur at any time during treatment. Bicarbonate decrements are usually mild-moderate (average decrease of 4 mEq/L at daily doses of 400 mg in adults and at approximately 6 mg/kg/day in pediatric patients); rarely, patients can experience severe decrements to values below 10 mEq/L. Conditions or therapies that predispose patients to acidosis (such as renal disease, severe respiratory disorders, status epilepticus, diarrhea, ketogenic diet, or specific drugs) may be additive to the bicarbonate lowering effects of topiramate.

In adults, the incidence of persistent treatment-emergent decreases in serum bicarbonate (levels of <20 mEq/L at two consecutive visits or at the final visit) in controlled clinical trials for adjunctive treatment of epilepsy was 32% for 400 mg/day, and 1% for placebo. Metabolic acidosis has been observed at doses as low as 50 mg/day. The incidence of persistent treatment-emergent decreases in serum bicarbonate in adults in the epilepsy controlled clinical trial for monotherapy was 15% for 50 mg/day and 25% for 400 mg/day. The incidence of a markedly abnormally low serum bicarbonate (i.e., absolute value <17 mEq/L and >5 mEq/L decrease from pretreatment) in the adjunctive therapy trials was 3% for 400 mg/day, and 0% for placebo and in the monotherapy trial was 1% for 50 mg/day and 7% for 400 mg/day. Serum bicarbonate levels have not been systematically evaluated at daily doses greater than 400 mg/day.

In pediatric patients (2 to 16 years of age), the incidence of persistent treatment-emergent decreases in serum bicarbonate in placebo-controlled trials for adjunctive treatment of Lennox-Gastaut syndrome or refractory partial onset seizures was 67% for TOPAMAX® (at approximately 6 mg/kg/day), and 10% for placebo. The incidence of a markedly abnormally low serum bicarbonate (i.e., absolute value <17 mEq/L and >5 mEq/L decrease from pretreatment) in these trials was 11% for TOPAMAX® and 0% for placebo. Cases of moderately severe metabolic acidosis have been reported in patients as young as 5 months old, especially at daily doses above 5 mg/kg/day.

Although not approved for use in patients under 2 years of age with partial onset seizures, a controlled trial that examined this population revealed that topiramate produced a metabolic acidosis that is notably greater in magnitude than that observed in controlled trials in older children and adults. The mean treatment difference (25 mg/kg/day topiramate-placebo) was -5.9 mEq/L for bicarbonate. The incidence of metabolic acidosis (defined by a serum bicarbonate <20 mEq/L) was 0% for placebo, 30% for 5 mg/kg/day, 50% for 15 mg/kg/day, and 45% for 25 mg/kg/day. The incidence of markedly abnormal changes (i.e., <17 mEq/L and >5 mEq/L decrease from baseline of ≥20 mEq/L) was 0% for placebo, 4% for 5 mg/kg/day, 5% for 15 mg/kg/day, and 5% for 25 mg/kg/day [see Use in Special Populations (8.4)].

In pediatric patients (6 to 15 years of age), the incidence of persistent treatment-emergent decreases in serum bicarbonate in the epilepsy controlled clinical trial for monotherapy was 9% for 50 mg/day and 25% for 400 mg/day. The incidence of a markedly abnormally low serum bicarbonate (i.e., absolute value <17 mEq/L and >5 mEq/L decrease from pretreatment) in this trial was 1% for 50 mg/day and 6% for 400 mg/day. In adult patients (≥16 years of age), the incidence of persistent treatment-emergent decreases in serum bicarbonate in the epilepsy controlled clinical trial for monotherapy was 14% for 50 mg/day and 25% for 400 mg/day. The incidence of a markedly abnormally low serum bicarbonate (i.e., absolute value <17 mEq/L and >5 mEq/L decrease from pretreatment) in this trial for adults was 1% for 50 mg/day and 6% for 400 mg/day.

The incidence of persistent treatment-emergent decreases in serum bicarbonate in placebo-controlled trials for adults for prophylaxis of migraine was 44% for 200 mg/day, 39% for 100 mg/day, 23% for 50 mg/day, and 7% for placebo. The incidence of a markedly abnormally low serum bicarbonate (i.e., absolute value <17 mEq/L and >5 mEq/L decrease from pretreatment) in these trials was 11% for 200 mg/day, 9% for 100 mg/day, 2% for 50 mg/day, and <1% for placebo.

Some manifestations of acute or chronic metabolic acidosis may include hyperventilation, nonspecific symptoms such as fatigue and anorexia, or more severe sequelae including cardiac arrhythmias or stupor. Chronic, untreated metabolic acidosis may increase the risk for nephrolithiasis or nephrocalcinosis, and may also result in osteomalacia (referred to as rickets in pediatric patients) and/or osteoporosis with an increased risk for fractures. Chronic metabolic acidosis in pediatric patients may also reduce growth rates. A reduction in growth rate may eventually decrease the maximal height achieved. The effect of topiramate on growth and bone-related sequelae has not been systematically investigated in long-term, placebo-controlled trials. Long-term, open-label treatment of infants/toddlers, with intractable partial epilepsy, for up to 1 year, showed reductions from baseline in Z SCORES for length, weight, and head circumference compared to age and sex-matched normative data, although these patients with epilepsy are likely to have different growth rates than normal infants. Reductions in Z SCORES for length and weight were correlated to the degree of acidosis [see Use in Specific Populations (8.4)]. Topiramate treatment that causes metabolic acidosis during pregnancy can possibly produce adverse effects on the fetus and might also cause metabolic acidosis in the neonate from possible transfer of topiramate to the fetus [see Warnings and Precautions (5.6) and Use in Specific Populations (8.1)].

Measurement of baseline and periodic serum bicarbonate during topiramate treatment is recommended. If metabolic acidosis develops and persists, consideration should be given to reducing the dose or discontinuing topiramate (using dose tapering). If the decision is made to continue patients on topiramate in the face of persistent acidosis, alkali treatment should be considered.

5.4 Suicidal Behavior and Ideation

Antiepileptic drugs (AEDs), including TOPAMAX®, increase the risk of suicidal thoughts or behavior in patients taking these drugs for any indication. Patients treated with any AED for any indication should be monitored for the emergence or worsening of depression, suicidal thoughts or behavior, and/or any unusual changes in mood or behavior.

Pooled analyses of 199 placebo-controlled clinical trials (mono- and adjunctive therapy) of 11 different AEDs showed that patients randomized to one of the AEDs had approximately twice the risk (adjusted Relative Risk 1.8, 95% CI:1.2, 2.7) of suicidal thinking or behavior compared to patients randomized to placebo. In these trials, which had a median treatment duration of 12 weeks, the estimated incidence rate of suicidal behavior or ideation among 27,863 AED-treated patients was 0.43%, compared to 0.24% among 16,029 placebo-treated patients, representing an increase of approximately one case of suicidal thinking or behavior for every 530 patients treated. There were four suicides in drug-treated patients in the trials and none in placebo-treated patients, but the number is too small to allow any conclusion about drug effect on suicide.

The increased risk of suicidal thoughts or behavior with AEDs was observed as early as one week after starting drug treatment with AEDs and persisted for the duration of treatment assessed. Because most trials included in the analysis did not extend beyond 24 weeks, the risk of suicidal thoughts or behavior beyond 24 weeks could not be assessed.

The risk of suicidal thoughts or behavior was generally consistent among drugs in the data analyzed. The finding of increased risk with AEDs of varying mechanisms of action and across a range of indications suggests that the risk applies to all AEDs used for any indication. The risk did not vary substantially by age (5 to 100 years) in the clinical trials analyzed.

Table 4 shows absolute and relative risk by indication for all evaluated AEDs.

Table 4: Risk by Indication for Antiepileptic Drugs in the Pooled Analysis
Indication | Placebo Patients with Events per 1000 Patients | Drug Patients with Events per 1000 Patients | Relative Risk: Incidence of Events in Drug Patients/Incidence in Placebo Patients | Risk Difference: Additional Drug Patients with Events per 1000 Patients
Epilepsy | 1.0 | 3.4 | 3.5 | 2.4
Psychiatric | 5.7 | 8.5 | 1.5 | 2.9
Other | 1.0 | 1.8 | 1.9 | 0.9
Total | 2.4 | 4.3 | 1.8 | 1.9

The relative risk for suicidal thoughts or behavior was higher in clinical trials for epilepsy than in clinical trials for psychiatric or other conditions, but the absolute risk differences were similar for the epilepsy and psychiatric indications.

Anyone considering prescribing TOPAMAX® or any other AED must balance the risk of suicidal thoughts or behavior with the risk of untreated illness. Epilepsy and many other illnesses for which AEDs are prescribed are themselves associated with morbidity and mortality and an increased risk of suicidal thoughts and behavior. Should suicidal thoughts and behavior emerge during treatment, the prescriber needs to consider whether the emergence of these symptoms in any given patient may be related to the illness being treated.

Patients, their caregivers, and families should be informed that AEDs increase the risk of suicidal thoughts and behavior and should be advised of the need to be alert for the emergence or worsening of the signs and symptoms of depression, any unusual changes in mood or behavior or the emergence of suicidal thoughts, or behavior or thoughts about self-harm. Behaviors of concern should be reported immediately to healthcare providers.

5.5 Cognitive/Neuropsychiatric Adverse Reactions

Adverse reactions most often associated with the use of TOPAMAX® were related to the central nervous system and were observed in both the epilepsy and migraine populations. In adults, the most frequent of these can be classified into three general categories: 1) Cognitive-related dysfunction (e.g., confusion, psychomotor slowing, difficulty with concentration/attention, difficulty with memory, speech or language problems, particularly word-finding difficulties); 2) Psychiatric/behavioral disturbances (e.g., depression or mood problems); and 3) Somnolence or fatigue.

Adult Patients

Cognitive-Related Dysfunction

The majority of cognitive-related adverse reactions were mild to moderate in severity, and they frequently occurred in isolation. Rapid titration rate and higher initial dose were associated with higher incidences of these reactions. Many of these reactions contributed to withdrawal from treatment [see Adverse Reactions (6)].

In the add-on epilepsy controlled trials (using rapid titration such as 100–200 mg/day weekly increments), the proportion of patients who experienced one or more cognitive-related adverse reactions was 42% for 200 mg/day, 41% for 400 mg/day, 52% for 600 mg/day, 56% for 800 and 1,000 mg/day, and 14% for placebo. These dose-related adverse reactions began with a similar frequency in the titration or in the maintenance phase, although in some patients the events began during titration and persisted into the maintenance phase. Some patients who experienced one or more cognitive-related adverse reactions in the titration phase had a dose-related recurrence of these reactions in the maintenance phase.

In the monotherapy epilepsy controlled trial, the proportion of patients who experienced one or more cognitive-related adverse reactions was 19% for TOPAMAX® 50 mg/day and 26% for 400 mg/day.

In the 6-month migraine prophylaxis controlled trials using a slower titration regimen (25 mg/day weekly increments), the proportion of patients who experienced one or more cognitive-related adverse reactions was 19% for TOPAMAX® 50 mg/day, 22% for 100 mg/day (the recommended dose), 28% for 200 mg/day, and 10% for placebo. These dose-related adverse reactions typically began in the titration phase and often persisted into the maintenance phase, but infrequently began in the maintenance phase. Some patients experienced a recurrence of one or more of these cognitive adverse reactions and this recurrence was typically in the titration phase. A relatively small proportion of topiramate-treated patients experienced more than one concurrent cognitive adverse reaction. The most common cognitive adverse reactions occurring together included difficulty with memory along with difficulty with concentration/attention, difficulty with memory along with language problems, and difficulty with concentration/attention along with language problems. Rarely, topiramate-treated patients experienced three concurrent cognitive reactions.

Psychiatric/Behavioral Disturbances

Psychiatric/behavioral disturbances (depression or mood) were dose-related for both the epilepsy and migraine populations [see Warnings and Precautions (5.4)].

Somnolence/Fatigue

Somnolence and fatigue were the adverse reactions most frequently reported during clinical trials of TOPAMAX® for adjunctive epilepsy. For the adjunctive epilepsy population, the incidence of somnolence did not differ substantially between 200 mg/day and 1,000 mg/day, but the incidence of fatigue was dose-related and increased at dosages above 400 mg/day. For the monotherapy epilepsy population in the 50 mg/day and 400 mg/day groups, the incidence of somnolence was dose-related (9% for the 50 mg/day group and 15% for the 400 mg/day group) and the incidence of fatigue was comparable in both treatment groups (14% each). For the migraine population, fatigue and somnolence were dose-related and more common in the titration phase.

Additional nonspecific CNS events commonly observed with topiramate in the add-on epilepsy population included dizziness or ataxia.

Pediatric Patients

In double-blind adjunctive therapy and monotherapy epilepsy clinical studies, the incidences of cognitive/neuropsychiatric adverse reactions in pediatric patients were generally lower than observed in adults. These reactions included psychomotor slowing, difficulty with concentration/attention, speech disorders/related speech problems, and language problems. The most frequently reported neuropsychiatric reactions in pediatric patients during adjunctive therapy double-blind studies were somnolence and fatigue. The most frequently reported neuropsychiatric reactions in pediatric patients in the 50 mg/day and 400 mg/day groups during the monotherapy double-blind study were headache, dizziness, anorexia, and somnolence.

No patients discontinued treatment due to any adverse reactions in the adjunctive epilepsy double-blind trials. In the monotherapy epilepsy double-blind trial, 1 pediatric patient (2%) in the 50 mg/day group and 7 pediatric patients (12%) in the 400 mg/day group discontinued treatment due to any adverse reactions. The most common adverse reaction associated with discontinuation of therapy was difficulty with concentration/attention; all occurred in the 400 mg/day group.

5.6 Fetal Toxicity

TOPAMAX® can cause fetal harm when administered to a pregnant woman. Data from pregnancy registries indicate that infants exposed to topiramate in utero have an increased risk for cleft lip and/or cleft palate (oral clefts). When multiple species of pregnant animals received topiramate at clinically relevant doses, structural malformations, including craniofacial defects, and reduced fetal weights occurred in offspring [see Use in Specific Populations (8.1)].

Consider the benefits and the risks of TOPAMAX® when administering this drug in women of childbearing potential, particularly when TOPAMAX® is considered for a condition not usually associated with permanent injury or death [see Use in Specific Populations (8.9) and Patient Counseling Information (17.8)]. TOPAMAX® should be used during pregnancy only if the potential benefit outweighs the potential risk. If this drug is used during pregnancy, or if the patient becomes pregnant while taking this drug, the patient should be apprised of the potential hazard to a fetus [see Use in Specific Populations (8.1) and (8.9)].

5.7 Withdrawal of Antiepileptic Drugs (AEDs)

In patients with or without a history of seizures or epilepsy, antiepileptic drugs, including TOPAMAX®, should be gradually withdrawn to minimize the potential for seizures or increased seizure frequency [see Clinical Studies (14)]. In situations where rapid withdrawal of TOPAMAX® is medically required, appropriate monitoring is recommended.

5.8 Sudden Unexplained Death in Epilepsy (SUDEP)

During the course of premarketing development of topiramate tablets, 10 sudden and unexplained deaths were recorded among a cohort of treated patients (2796 subject years of exposure). This represents an incidence of 0.0035 deaths per patient year. Although this rate exceeds that expected in a healthy population matched for age and sex, it is within the range of estimates for the incidence of sudden unexplained deaths in patients with epilepsy not receiving TOPAMAX® (ranging from 0.0005 for the general population of patients with epilepsy, to 0.003 for a clinical trial population similar to that in the TOPAMAX® program, to 0.005 for patients with refractory epilepsy).

5.9 Hyperammonemia and Encephalopathy (Without and With Concomitant Valproic Acid [VPA] Use)

Hyperammonemia/Encephalopathy Without Concomitant Valproic Acid (VPA)

Topiramate treatment has produced hyperammonemia (in some instances dose-related) in clinical investigational programs of adolescents (12–16 years) who were treated with topiramate monotherapy for migraine prophylaxis (incidence above the upper limit of normal, 22% for placebo, 26% for 50 mg/day, 41% for 100 mg/day) and in very young pediatric patients (1–24 months) who were treated with adjunctive topiramate for partial onset epilepsy (8% for placebo, 10% for 5 mg/kg/day, 0% for 15 mg/kg/day, 9% for 25 mg/kg/day). TOPAMAX® is not approved as monotherapy for migraine prophylaxis in adolescent patients or as adjunctive treatment of partial onset seizures in pediatric patients less than 2 years old. In some patients, ammonia was markedly increased (≥50% above upper limit of normal). In adolescent patients, the incidence of markedly increased hyperammonemia was 6% for placebo, 6% for 50 mg, and 12% for 100 mg topiramate daily. The hyperammonemia associated with topiramate treatment occurred with and without encephalopathy in placebo-controlled trials and in an open-label, extension trial. Dose-related hyperammonemia was also observed in the extension trial in pediatric patients up to 2 years old. Clinical symptoms of hyperammonemic encephalopathy often include acute alterations in level of consciousness and/or cognitive function with lethargy or vomiting.

Hyperammonemia with and without encephalopathy has also been observed in post-marketing reports in patients who were taking topiramate without concomitant valproic acid (VPA).

Hyperammonemia/Encephalopathy With Concomitant Valproic Acid (VPA)

Concomitant administration of topiramate and valproic acid (VPA) has been associated with hyperammonemia with or without encephalopathy in patients who have tolerated either drug alone based upon post-marketing reports. Although hyperammonemia may be asymptomatic, clinical symptoms of hyperammonemic encephalopathy often include acute alterations in level of consciousness and/or cognitive function with lethargy or vomiting. In most cases, symptoms and signs abated with discontinuation of either drug. This adverse reaction is not due to a pharmacokinetic interaction.

Although TOPAMAX® is not indicated for use in infants/toddlers (1–24 months), VPA clearly produced a dose-related increase in the incidence of treatment-emergent hyperammonemia (above the upper limit of normal, 0% for placebo, 12% for 5 mg/kg/day, 7% for 15 mg/kg/day, 17% for 25 mg/kg/day) in an investigational program. Markedly increased, dose-related hyperammonemia (0% for placebo and 5 mg/kg/day, 7% for 15 mg/kg/day, 8% for 25 mg/kg/day) also occurred in these infants/toddlers. Dose-related hyperammonemia was similarly observed in a long-term extension trial in these very young, pediatric patients [see Use in Specific Populations (8.4)].

Hyperammonemia with and without encephalopathy has also been observed in post-marketing reports in patients taking topiramate with VPA.

The hyperammonemia associated with topiramate treatment appears to be more common when topiramate is used concomitantly with VPA.

Monitoring for Hyperammonemia

Patients with inborn errors of metabolism or reduced hepatic mitochondrial activity may be at an increased risk for hyperammonemia with or without encephalopathy. Although not studied, topiramate treatment or an interaction of concomitant topiramate and valproic acid treatment may exacerbate existing defects or unmask deficiencies in susceptible persons.

In patients who develop unexplained lethargy, vomiting, or changes in mental status associated with any topiramate treatment, hyperammonemic encephalopathy should be considered and an ammonia level should be measured.

5.10 Kidney Stones

A total of 32/2086 (1.5%) of adults exposed to topiramate during its adjunctive epilepsy therapy development reported the occurrence of kidney stones, an incidence about 2 to 4 times greater than expected in a similar, untreated population. In the double-blind monotherapy epilepsy study, a total of 4/319 (1.3%) of adults exposed to topiramate reported the occurrence of kidney stones. As in the general population, the incidence of stone formation among topiramate-treated patients was higher in men. Kidney stones have also been reported in pediatric patients. During long-term (up to 1 year) topiramate treatment in an open-label extension study of 284 pediatric patients 1–24 months old with epilepsy, 7% developed kidney or bladder stones that were diagnosed clinically or by sonogram. TOPAMAX® is not approved for pediatric patients less than 2 years old [see Use in Specific Populations (8.4)].

An explanation for the association of TOPAMAX® and kidney stones may lie in the fact that topiramate is a carbonic anhydrase inhibitor. Carbonic anhydrase inhibitors (e.g., zonisamide, acetazolamide, or dichlorphenamide) can promote stone formation by reducing urinary citrate excretion and by increasing urinary pH [see Warnings and Precautions (5.3)]. The concomitant use of TOPAMAX® with any other drug producing metabolic acidosis, or potentially in patients on a ketogenic diet, may create a physiological environment that increases the risk of kidney stone formation, and should therefore be avoided.

Increased fluid intake increases the urinary output, lowering the concentration of substances involved in stone formation. Hydration is recommended to reduce new stone formation.

5.11 Hypothermia with Concomitant Valproic Acid (VPA) Use

Hypothermia, defined as an unintentional drop in body core temperature to <35°C (95°F), has been reported in association with topiramate use with concomitant valproic acid (VPA) both in conjunction with hyperammonemia and in the absence of hyperammonemia. This adverse reaction in patients using concomitant topiramate and valproate can occur after starting topiramate treatment or after increasing the daily dose of topiramate [see Drug Interactions (7.1)]. Consideration should be given to stopping topiramate or valproate in patients who develop hypothermia, which may be manifested by a variety of clinical abnormalities including lethargy, confusion, coma, and significant alterations in other major organ systems such as the cardiovascular and respiratory systems. Clinical management and assessment should include examination of blood ammonia levels.

5.12 Paresthesia

Paresthesia (usually tingling of the extremities), an effect associated with the use of other carbonic anhydrase inhibitors, appears to be a common effect of TOPAMAX®. Paresthesia was more frequently reported in the monotherapy epilepsy trials and migraine prophylaxis trials than in the adjunctive therapy epilepsy trials. In the majority of instances, paresthesia did not lead to treatment discontinuation.

5.13 Adjustment of Dose in Renal Failure

The major route of elimination of unchanged topiramate and its metabolites is via the kidney. Dosage adjustment may be required in patients with reduced renal function [see Dosage and Administration (2.4)].

5.14 Decreased Hepatic Function

In hepatically impaired patients, TOPAMAX® should be administered with caution as the clearance of topiramate may be decreased [see Dosage and Administration (2.7)].

5.15 Monitoring: Laboratory Tests

Topiramate treatment was associated with changes in several clinical laboratory analytes in randomized, double-blind, placebo-controlled studies.

Topiramate treatment causes non-anion gap, hyperchloremic metabolic acidosis manifested by a decrease in serum bicarbonate and an increase in serum chloride. Measurement of baseline and periodic serum bicarbonate during TOPAMAX® treatment is recommended [see Warnings and Precautions (5.3)].

Controlled trials of adjunctive topiramate treatment of adults for partial onset seizures showed an increased incidence of markedly decreased serum phosphorus (6% topiramate, 2% placebo), markedly increased serum alkaline phosphatase (3% topiramate, 1% placebo), and decreased serum potassium (0.4 % topiramate, 0.1 % placebo). The clinical significance of these abnormalities has not been clearly established.

Changes in several clinical laboratory values (i.e., increased creatinine, BUN, alkaline phosphatase, total protein, total eosinophil count, and decreased potassium) have been observed in a clinical investigational program in very young (<2 years) pediatric patients who were treated with adjunctive topiramate for partial onset seizures [see Use in Specific Populations (8.4)].

Topiramate treatment produced a dose-related increased shift in serum creatinine from normal at baseline to an increased value at the end of 4 months treatment in adolescent patients (ages 12–16 years) who were treated for migraine prophylaxis in a double-blind, placebo-controlled study.

TOPAMAX® treatment with or without concomitant valproic acid (VPA) can cause hyperammonemia with or without encephalopathy [see Warnings and Precautions (5.9)].

6 ADVERSE REACTIONS

Because clinical trials are conducted under widely varying conditions, adverse reaction rates observed in the clinical trials of a drug cannot be directly compared to rates in the clinical trials of another drug and may not reflect the rates observed in practice.

The following adverse reactions are discussed in more detail in other sections of the labeling:

- Acute Myopia and Secondary Angle Closure [see Warnings and Precautions (5.1)]
- Oligohidrosis and Hyperthermia [see Warnings and Precautions (5.2)]
- Metabolic Acidosis [see Warnings and Precautions (5.3)]
- Suicidal Behavior and Ideation [see Warnings and Precautions (5.4)]
- Cognitive/Neuropsychiatric Adverse Reactions [see Warnings and Precautions (5.5)]
- Fetal Toxicity [see Warnings and Precautions (5.6) and Use in Specific Populations (8.1)]
- Withdrawal of Antiepileptic Drugs (AEDs) [see Warnings and Precautions (5.7)]
- Sudden Unexplained Death in Epilepsy (SUDEP) [see Warnings and Precautions (5.8)]
- Hyperammonemia and Encephalopathy (Without and With Concomitant Valproic Acid [VPA] Use [see Warnings and Precautions (5.9)]
- Kidney Stones [see Warnings and Precautions (5.10)]
- Hypothermia with Concomitant Valproic Acid (VPA) Use [see Warnings and Precautions (5.11)]
- Paresthesia [see Warnings and Precautions (5.12)]

The data described in the following sections were obtained using TOPAMAX® (topiramate) Tablets.

6.1 Monotherapy Epilepsy

Adults ≥16 Years

The adverse reactions in the controlled trial that occurred most commonly in adults in the 400 mg/day TOPAMAX® group and at a rate higher (≥ 5 %) than in the 50 mg/day group were: paresthesia, weight decrease, anorexia, somnolence, and difficulty with memory (see Table 5).

Approximately 21% of the 159 adult patients in the 400 mg/day group who received topiramate as monotherapy in the controlled clinical trial discontinued therapy due to adverse reactions. The most common (≥ 2% more frequent than low-dose 50 mg/day TOPAMAX®) adverse reactions causing discontinuation in this trial were difficulty with memory, fatigue, asthenia, insomnia, somnolence, and paresthesia.

Pediatric Patients 6 to <16 Years of Age

The adverse reactions in the controlled trial that occurred most commonly in pediatric patients in the 400 mg/day TOPAMAX® group and at a rate higher (≥ 5%) than in the 50 mg/day group were fever, weight decrease, mood problems, cognitive problems, infection, flushing, and paresthesia (see Table 5).

Approximately 14% of the 77 pediatric patients in the 400 mg/day group who received TOPAMAX® as monotherapy in the controlled clinical trial discontinued therapy due to adverse reactions. The most common (> 2% more frequent than low-dose 50 mg/day TOPAMAX®) adverse reactions resulting in discontinuation in this trial were difficulty with concentration/attention, fever, flushing, and confusion.

Table 5: Incidence of Treatment-Emergent Adverse Reactions in Monotherapy Epilepsy Where the Rate Was at Least 2% in Any TOPAMAX® Group and the Rate in the 400 mg/day TOPAMAX® Group Was Greater Than the Rate in the 50 mg/day TOPAMAX® Group for Adults (≥16 Years) and Pediatric (6 to <16 Years) Patients in Study TOPMAX-EPMN-106
 | Age Group
 | Pediatric (6 to <16 Years) |  | Adult (Age ≥16 Years)
 | TOPAMAX® Daily Dosage Group (mg/day)
 | 50 | 400 | 50 | 400
Body System | (N=74) | (N=77) | (N=160) | (N=159)
Adverse Reaction | % [Percentages calculated with the number of subjects in each group as denominator] | % | % | %
Body as a Whole - General Disorders
Asthenia | 0 | 3 | 4 | 6
Chest pain |  |  | 1 | 2
Fever | 1 | 12
Leg pain |  |  | 2 | 3
Central & Peripheral Nervous System Disorders
Ataxia |  |  | 3 | 4
Dizziness |  |  | 13 | 14
Hypertonia |  |  | 0 | 3
Hypoesthesia |  |  | 4 | 5
Muscle contractions involuntary | 0 | 3
Paresthesia | 3 | 12 | 21 | 40
Vertigo | 0 | 3
Gastro-Intestinal System Disorders
Constipation |  |  | 1 | 4
Diarrhea | 8 | 9
Gastritis |  |  | 0 | 3
Gastroesophageal reflux |  |  | 1 | 2
Dry mouth |  |  | 1 | 3
Liver and Biliary System Disorders
Gamma-GT increased |  |  | 1 | 3
Metabolic and Nutritional Disorders
Weight decrease | 7 | 17 | 6 | 17
Platelet, Bleeding & Clotting Disorders
Epistaxis | 0 | 4
Psychiatric Disorders
Anorexia |  |  | 4 | 14
Anxiety |  |  | 4 | 6
Cognitive problems | 1 | 6 | 1 | 4
Confusion | 0 | 3
Depression | 0 | 3 | 7 | 9
Difficulty with concentration/attention | 7 | 10 | 7 | 8
Difficulty with memory | 1 | 3 | 6 | 11
Insomnia |  |  | 8 | 9
Libido decreased |  |  | 0 | 3
Mood problems | 1 | 8 | 2 | 5
Personality disorder(behavior problems) | 0 | 3
Psychomotor slowing |  |  | 3 | 5
Somnolence |  |  | 10 | 15
Red Blood Cell Disorders
Anemia | 1 | 3
Reproductive Disorders, Female
Intermenstrual Bleeding | 0 | 3
Vaginal Hemorrhage |  |  | 0 | 3
Resistance Mechanism Disorders
Infection | 3 | 8 | 2 | 3
Infection viral | 3 | 6 | 6 | 8
Respiratory System Disorders
Bronchitis | 1 | 5 | 3 | 4
Dyspnea |  |  | 1 | 2
Rhinitis | 5 | 6 | 2 | 4
Sinusitis | 1 | 4
Upper respiratory tract infection | 16 | 18
Skin and Appendages Disorders
Acne |  |  | 2 | 3
Alopecia | 1 | 4 | 3 | 4
Pruritus |  |  | 1 | 4
Rash | 3 | 4 | 1 | 4
Special Senses Other, Disorders
Taste perversion |  |  | 3 | 5
Urinary System Disorders
Cystitis |  |  | 1 | 3
Dysuria |  |  | 0 | 2
Micturition frequency | 0 | 3 | 0 | 2
Renal calculus |  |  | 0 | 3
Urinary incontinence | 1 | 3
Urinary tract infection |  |  | 1 | 2
Vascular (Extracardiac) Disorders
Flushing | 0 | 5

6.2 Adjunctive Therapy Epilepsy

The most commonly observed adverse reactions associated with the use of TOPAMAX® at dosages of 200 to 400 mg/day in controlled trials in adults with partial onset seizures, primary generalized tonic-clonic seizures, or Lennox-Gastaut syndrome, that were seen at greater frequency in TOPAMAX®-treated patients and did not appear to be dose-related were somnolence, dizziness, ataxia, speech disorders and related speech problems, psychomotor slowing, abnormal vision, difficulty with memory, paresthesia and diplopia (see Table 6). The most common dose-related adverse reactions at dosages of 200 to 1,000 mg/day were fatigue, nervousness, difficulty with concentration or attention, confusion, depression, anorexia, language problems, anxiety, mood problems, and weight decrease (see Table 8).

Adverse reactions associated with the use of TOPAMAX® at dosages of 5 to 9 mg/kg/day in controlled trials in pediatric patients with partial onset seizures, primary generalized tonic-clonic seizures, or Lennox-Gastaut syndrome, that were seen at greater frequency in TOPAMAX®- treated patients were fatigue, somnolence, anorexia, nervousness, difficulty with concentration/attention, difficulty with memory, aggressive reaction, and weight decrease (see Table 9).

In controlled clinical trials in adults, 11% of patients receiving TOPAMAX® 200 to 400 mg/day as adjunctive therapy discontinued due to adverse reactions. This rate appeared to increase at dosages above 400 mg/day. Adverse reactions associated with discontinuing therapy included somnolence, dizziness, anxiety, difficulty with concentration or attention, fatigue, and paresthesia and increased at dosages above 400 mg/day. None of the pediatric patients who received TOPAMAX® adjunctive therapy at 5 to 9 mg/kg/day in controlled clinical trials discontinued due to adverse reactions.

Approximately 28% of the 1757 adults with epilepsy who received TOPAMAX® at dosages of 200 to 1,600 mg/day in clinical studies discontinued treatment because of adverse reactions; an individual patient could have reported more than one adverse reaction. These adverse reactions were psychomotor slowing (4.0%), difficulty with memory (3.2%), fatigue (3.2%), confusion (3.1%), somnolence (3.2%), difficulty with concentration/attention (2.9%), anorexia (2.7%), depression (2.6%), dizziness (2.5%), weight decrease (2.5%), nervousness (2.3%), ataxia (2.1%), and paresthesia (2.0%). Approximately 11% of the 310 pediatric patients who received TOPAMAX® at dosages up to 30 mg/kg/day discontinued due to adverse reactions. Adverse reactions associated with discontinuing therapy included aggravated convulsions (2.3%), difficulty with concentration/attention (1.6%), language problems (1.3%), personality disorder (1.3%), and somnolence (1.3%).

6.3 Incidence in Epilepsy Controlled Clinical Trials – Adjunctive Therapy – Partial Onset Seizures, Primary Generalized Tonic-Clonic Seizures, and Lennox-Gastaut Syndrome

Table 6 lists treatment-emergent adverse reactions that occurred in at least 1% of adults treated with 200 to 400 mg/day TOPAMAX® in controlled trials that were numerically more common at this dose than in the patients treated with placebo. In general, most patients who experienced adverse reactions during the first eight weeks of these trials no longer experienced them by their last visit. Table 9 lists treatment-emergent adverse reactions that occurred in at least 1% of pediatric patients treated with 5 to 9 mg/kg TOPAMAX® in controlled trials that were numerically more common than in patients treated with placebo.

The prescriber should be aware that these data were obtained when TOPAMAX® was added to concurrent antiepileptic drug therapy and cannot be used to predict the frequency of adverse reactions in the course of usual medical practice where patient characteristics and other factors may differ from those prevailing during clinical studies. Similarly, the cited frequencies cannot be directly compared with data obtained from other clinical investigations involving different treatments, uses, or investigators. Inspection of these frequencies, however, does provide the prescribing physician with a basis to estimate the relative contribution of drug and non-drug factors to the adverse reaction incidences in the population studied.

6.4 Other Adverse Reactions Observed During Double-Blind Epilepsy Adjunctive Therapy Trials

Other adverse reactions that occurred in more than 1% of adults treated with 200 to 400 mg of TOPAMAX® in placebo-controlled epilepsy trials but with equal or greater frequency in the placebo group were headache, injury, anxiety, rash, pain, convulsions aggravated, coughing, fever, diarrhea, vomiting, muscle weakness, insomnia, personality disorder, dysmenorrhea, upper respiratory tract infection, and eye pain.

Table 6: Incidence of Treatment-Emergent Adverse Reactions in Placebo-Controlled, Add-On Epilepsy Trials in Adults, Where Incidence Was >1% in Any TOPAMAX® Group and Greater Than the Rate in Placebo-Treated Patients
 |  | TOPAMAX® Dosage (mg/day)
Body System/ | Placebo | 200–400 | 600–1,000
Adverse Reaction | (N=291) | (N=183) | (N=414)
Body as a Whole-General Disorders
Fatigue | 13 | 15 | 30
Asthenia | 1 | 6 | 3
Back pain | 4 | 5 | 3
Chest pain | 3 | 4 | 2
Influenza-like symptoms | 2 | 3 | 4
Leg pain | 2 | 2 | 4
Hot flushes | 1 | 2 | 1
Allergy | 1 | 2 | 3
Edema | 1 | 2 | 1
Body odor | 0 | 1 | 0
Rigors | 0 | 1 | <1
Central & Peripheral Nervous System Disorders
Dizziness | 15 | 25 | 32
Ataxia | 7 | 16 | 14
Speech disorders/Related speech problems | 2 | 13 | 11
Paresthesia | 4 | 11 | 19
Nystagmus | 7 | 10 | 11
Tremor | 6 | 9 | 9
Language problems | 1 | 6 | 10
Coordination abnormal | 2 | 4 | 4
Hypoesthesia | 1 | 2 | 1
Gait abnormal | 1 | 3 | 2
Muscle contractions involuntary | 1 | 2 | 2
Stupor | 0 | 2 | 1
Vertigo | 1 | 1 | 2
Gastro-Intestinal System Disorders
Nausea | 8 | 10 | 12
Dyspepsia | 6 | 7 | 6
Abdominal pain | 4 | 6 | 7
Constipation | 2 | 4 | 3
Gastroenteritis | 1 | 2 | 1
Dry mouth | 1 | 2 | 4
Gingivitis | <1 | 1 | 1
GI disorder | <1 | 1 | 0
Hearing and Vestibular Disorders
Hearing decreased | 1 | 2 | 1
Metabolic and Nutritional Disorders
Weight decrease | 3 | 9 | 13
Muscle-Skeletal System Disorders
Myalgia | 1 | 2 | 2
Skeletal pain | 0 | 1 | 0
Platelet, Bleeding, & Clotting Disorders
Epistaxis | 1 | 2 | 1
Psychiatric Disorders
Somnolence | 12 | 29 | 28
Nervousness | 6 | 16 | 19
Psychomotor slowing | 2 | 13 | 21
Difficulty with memory | 3 | 12 | 14
Anorexia | 4 | 10 | 12
Confusion | 5 | 11 | 14
Depression | 5 | 5 | 13
Difficulty with concentration/attention | 2 | 6 | 14
Mood problems | 2 | 4 | 9
Agitation | 2 | 3 | 3
Aggressive reaction | 2 | 3 | 3
Emotional lability | 1 | 3 | 3
Cognitive problems | 1 | 3 | 3
Libido decreased | 1 | 2 | <1
Apathy | 1 | 1 | 3
Depersonalization | 1 | 1 | 2
Reproductive Disorders, Female
Breast pain | 2 | 4 | 0
Amenorrhea | 1 | 2 | 2
Menorrhagia | 0 | 2 | 1
Menstrual disorder | 1 | 2 | 1
Reproductive Disorders, Male
Prostatic disorder | <1 | 2 | 0
Resistance Mechanism Disorders
Infection | 1 | 2 | 1
Infection viral | 1 | 2 | <1
Moniliasis | <1 | 1 | 0
Respiratory System Disorders
Pharyngitis | 2 | 6 | 3
Rhinitis | 6 | 7 | 6
Sinusitis | 4 | 5 | 6
Dyspnea | 1 | 1 | 2
Skin and Appendages Disorders
Skin disorder | <1 | 2 | 1
Sweating increased | <1 | 1 | <1
Rash erythematous | <1 | 1 | <1
Special Sense Other, Disorders
Taste perversion | 0 | 2 | 4
Urinary System Disorders
Hematuria | 1 | 2 | <1
Urinary tract infection | 1 | 2 | 3
Micturition frequency | 1 | 1 | 2
Urinary incontinence | <1 | 2 | 1
Urine abnormal | 0 | 1 | <1
Vision Disorders
Vision abnormal | 2 | 13 | 10
Diplopia | 5 | 10 | 10
White Cell and RES Disorders
Leukopenia | 1 | 2 | 1

6.5 Incidence in Study 119 – Add-On Therapy– Adults with Partial Onset Seizures

Study 119 was a randomized, double-blind, add-on/adjunctive, placebo-controlled, parallel group study with 3 treatment arms: 1) placebo; 2) TOPAMAX® 200 mg/day with a 25 mg/day starting dose, increased by 25 mg/day each week for 8 weeks until the 200 mg/day maintenance dose was reached; and 3) TOPAMAX® 200 mg/day with a 50 mg/day starting dose, increased by 50 mg/day each week for 4 weeks until the 200 mg/day maintenance dose was reached. All patients were maintained on concomitant carbamazepine with or without another concomitant antiepileptic drug.

The incidence of adverse reactions (Table 7) did not differ significantly between the 2 TOPAMAX® regimens. Because the frequencies of adverse reactions reported in this study were markedly lower than those reported in the previous epilepsy studies, they cannot be directly compared with data obtained in other studies.

Table 7: Incidence of Treatment-Emergent Adverse Reactions in Study 119, Where Incidence Was ≥ 2% in the TOPAMAX® Group and Greater Than the Rate in Placebo-Treated Patients
 |  | TOPAMAX® Dosage (mg/day)
Body System/ | Placebo | 200
Adverse Reaction | (N=92) | (N=171)
Body as a Whole-General Disorders
Fatigue | 4 | 9
Chest pain | 1 | 2
Cardiovascular Disorders, General
Hypertension | 0 | 2
Central & Peripheral Nervous System Disorders
Paresthesia | 2 | 9
Dizziness | 4 | 7
Tremor | 2 | 3
Hypoesthesia | 0 | 2
Leg cramps | 0 | 2
Language problems | 0 | 2
Gastro-Intestinal System Disorders
Abdominal pain | 3 | 5
Constipation | 0 | 4
Diarrhea | 1 | 2
Dyspepsia | 0 | 2
Dry mouth | 0 | 2
Hearing and Vestibular Disorders
Tinnitus | 0 | 2
Metabolic and Nutritional Disorders
Weight decrease | 4 | 8
Psychiatric Disorders
Somnolence | 9 | 15
Anorexia | 7 | 9
Nervousness | 2 | 9
Difficulty with concentration/attention | 0 | 5
Insomnia | 3 | 4
Difficulty with memory | 1 | 2
Aggressive reaction | 0 | 2
Respiratory System Disorders
Rhinitis | 0 | 4
Urinary System Disorders
Cystitis | 0 | 2
Vision Disorders
Diplopia | 0 | 2
Vision abnormal | 0 | 2

Table 8: Incidence (%) of Dose-Related Adverse Reactions From Placebo-Controlled, Add-On Trials in Adults With Partial Onset Seizures [Dose-response studies were not conducted for other adult indications or for pediatric indications.]
 |  | TOPAMAX® Dosage (mg/day)
 | Placebo | 200 | 400 | 600 – 1,000
Adverse Reaction | (N = 216) | (N = 45) | (N = 68) | (N = 414)
Fatigue | 13 | 11 | 12 | 30
Nervousness | 7 | 13 | 18 | 19
Difficulty with concentration/attention | 1 | 7 | 9 | 14
Confusion | 4 | 9 | 10 | 14
Depression | 6 | 9 | 7 | 13
Anorexia | 4 | 4 | 6 | 12
Language problems | <1 | 2 | 9 | 10
Anxiety | 6 | 2 | 3 | 10
Mood problems | 2 | 0 | 6 | 9
Weight decrease | 3 | 4 | 9 | 13

Table 9: Incidence (%) of Treatment-Emergent Adverse Reactions in Placebo-Controlled, Add-On Epilepsy Trials in Pediatric Patients (Ages 2 –16 Years), (Reactions That Occurred in at Least 1% of TOPAMAX®-Treated Patients and Occurred More Frequently in TOPAMAX®-Treated Than Placebo-Treated Patients)
Body System/ | Placebo | TOPAMAX®
Adverse Reaction | (N=101) | (N=98)
Body as a Whole - General Disorders
Fatigue | 5 | 16
Injury | 13 | 14
Allergic reaction | 1 | 2
Back pain | 0 | 1
Pallor | 0 | 1
Cardiovascular Disorders, General
Hypertension | 0 | 1
Central & Peripheral Nervous System Disorders
Gait abnormal | 5 | 8
Ataxia | 2 | 6
Hyperkinesia | 4 | 5
Dizziness | 2 | 4
Speech disorders/Related speech problems | 2 | 4
Hyporeflexia | 0 | 2
Convulsions grand mal | 0 | 1
Fecal incontinence | 0 | 1
Paresthesia | 0 | 1
Gastro-Intestinal System Disorders
Nausea | 5 | 6
Saliva increased | 4 | 6
Constipation | 4 | 5
Gastroenteritis | 2 | 3
Dysphagia | 0 | 1
Flatulence | 0 | 1
Gastroesophageal reflux | 0 | 1
Glossitis | 0 | 1
Gum hyperplasia | 0 | 1
Heart Rate and Rhythm Disorders
Bradycardia | 0 | 1
Metabolic and Nutritional Disorders
Weight decrease | 1 | 9
Thirst | 1 | 2
Hypoglycemia | 0 | 1
Weight increase | 0 | 1
Platelet, Bleeding, & Clotting Disorders
Purpura | 4 | 8
Epistaxis | 1 | 4
Hematoma | 0 | 1
Prothrombin increased | 0 | 1
Thrombocytopenia | 0 | 1
Psychiatric Disorders
Somnolence | 16 | 26
Anorexia | 15 | 24
Nervousness | 7 | 14
Personality disorder (behavior problems) | 9 | 11
Difficulty with concentration/attention | 2 | 10
Aggressive reaction | 4 | 9
Insomnia | 7 | 8
Difficulty with memory | 0 | 5
Confusion | 3 | 4
Psychomotor slowing | 2 | 3
Appetite increased | 0 | 1
Neurosis | 0 | 1
Reproductive Disorders, Female
Leukorrhea | 0 | 2
Resistance Mechanism Disorders
Infection viral | 3 | 7
Respiratory System Disorders
Pneumonia | 1 | 5
Respiratory disorder | 0 | 1
Skin and Appendages Disorders
Skin disorder | 2 | 3
Alopecia | 1 | 2
Dermatitis | 0 | 2
Hypertrichosis | 1 | 2
Rash erythematous | 0 | 2
Eczema | 0 | 1
Seborrhea | 0 | 1
Skin discoloration | 0 | 1
Urinary System Disorders
Urinary incontinence | 2 | 4
Nocturia | 0 | 1
Vision Disorders
Eye abnormality | 1 | 2
Vision abnormal | 1 | 2
Diplopia | 0 | 1
Lacrimation abnormal | 0 | 1
Myopia | 0 | 1
White Cell and RES Disorders
Leukopenia | 0 | 2

6.6 Other Adverse Reactions Observed During All Epilepsy Clinical Trials

TOPAMAX® has been administered to 2246 adults and 427 pediatric patients with epilepsy during all clinical studies, only some of which were placebo-controlled. During these studies, all adverse reactions were recorded by the clinical investigators using terminology of their own choosing. To provide a meaningful estimate of the proportion of individuals having adverse reactions, similar types of reactions were grouped into a smaller number of standardized categories using modified WHOART dictionary terminology. The frequencies presented represent the proportion of patients who experienced a reaction of the type cited on at least one occasion while receiving TOPAMAX®. Reported reactions are included except those already listed in the previous tables or text, those too general to be informative, and those not reasonably associated with the use of the drug.

Reactions are classified within body system categories and enumerated in order of decreasing frequency using the following definitions: frequent occurring in at least 1/100 patients; infrequent occurring in 1/100 to 1/1000 patients; rare occurring in fewer than 1/1000 patients.

Autonomic Nervous System Disorders: Infrequent: vasodilation.

Body as a Whole: Frequent: syncope. Infrequent: abdomen enlarged. Rare: alcohol intolerance.

Cardiovascular Disorders, General: Infrequent: hypotension, postural hypotension, angina pectoris.

Central & Peripheral Nervous System Disorders: Infrequent: neuropathy, apraxia, hyperesthesia, dyskinesia, dysphonia, scotoma, ptosis, dystonia, visual field defect, encephalopathy, EEG abnormal. Rare: upper motor neuron lesion, cerebellar syndrome, tongue paralysis.

Gastrointestinal System Disorders: Infrequent: hemorrhoids, stomatitis, melena, gastritis, esophagitis. Rare: tongue edema.

Heart Rate and Rhythm Disorders: Infrequent: AV block.

Liver and Biliary System Disorders: Infrequent: SGPT increased, SGOT increased.

Metabolic and Nutritional Disorders: Infrequent: dehydration, hypocalcemia, hyperlipemia, hyperglycemia, xerophthalmia, diabetes mellitus. Rare: hypernatremia, hyponatremia, hypocholesterolemia, creatinine increased.

Musculoskeletal System Disorders: Frequent: arthralgia. Infrequent: arthrosis.

Neoplasms: Infrequent: thrombocythemia. Rare: polycythemia.

Platelet, Bleeding, and Clotting Disorders: Infrequent: gingival bleeding, pulmonary embolism.

Psychiatric Disorders: Frequent: impotence, hallucination, psychosis, suicide attempt. Infrequent: euphoria, paranoid reaction, delusion, paranoia, delirium, abnormal dreaming. Rare: libido increased, manic reaction.

Red Blood Cell Disorders: Frequent: anemia. Rare: marrow depression, pancytopenia.

Reproductive Disorders, Male: Infrequent: ejaculation disorder, breast discharge.

Skin and Appendages Disorders: Infrequent: urticaria, photosensitivity reaction, abnormal hair texture. Rare: chloasma.

Special Senses Other, Disorders: Infrequent: taste loss, parosmia.

Urinary System Disorders: Infrequent: urinary retention, face edema, renal pain, albuminuria, polyuria, oliguria.

Vascular (Extracardiac) Disorders: Infrequent: flushing, deep vein thrombosis, phlebitis. Rare: vasospasm.

Vision Disorders: Frequent: conjunctivitis. Infrequent: abnormal accommodation, photophobia, strabismus. Rare: mydriasis, iritis.

White Cell and Reticuloendothelial System Disorders: Infrequent: lymphadenopathy, eosinophilia, lymphopenia, granulocytopenia. Rare: lymphocytosis.

6.7 Migraine

In the four multicenter, randomized, double-blind, placebo-controlled, parallel group migraine prophylaxis clinical trials, most of the adverse reactions with TOPAMAX® were mild or moderate in severity. Most adverse reactions occurred more frequently during the titration period than during the maintenance period.

Table 10 includes those adverse reactions reported for patients in the placebo-controlled trials where the incidence in any TOPAMAX® treatment group was at least 2% and was greater than that for placebo patients.

Table 10: Incidence of Treatment-Emergent Adverse Reactions in Placebo-Controlled, Migraine Trials Where Incidence Was ≥2 % in Any TOPAMAX® Group and Greater Than the Rate in Placebo-Treated Patients
 |  | TOPAMAX® Dosage (mg/day)
Body System/ | Placebo | 50 | 100 | 200
Adverse Reaction | (N=445) | (N=235) | (N=386) | (N=514)
Body as a Whole-General Disorders
Fatigue | 11 | 14 | 15 | 19
Injury | 7 | 9 | 6 | 6
Asthenia | 1 | <1 | 2 | 2
Fever | 1 | 1 | 1 | 2
Influenza-like symptoms | <1 | <1 | <1 | 2
Allergy | <1 | 2 | <1 | <1
Central & Peripheral Nervous System Disorders
Paresthesia | 6 | 35 | 51 | 49
Dizziness | 10 | 8 | 9 | 12
Hypoesthesia | 2 | 6 | 7 | 8
Language problems | 2 | 7 | 6 | 7
Involuntary muscle contractions | 1 | 2 | 2 | 4
Ataxia | <1 | 1 | 2 | 1
Speech disorders/Related speech problems | <1 | 1 | <1 | 2
Gastro-Intestinal System Disorders
Nausea | 8 | 9 | 13 | 14
Diarrhea | 4 | 9 | 11 | 11
Abdominal pain | 5 | 6 | 6 | 7
Dyspepsia | 3 | 4 | 5 | 3
Dry mouth | 2 | 2 | 3 | 5
Vomiting | 2 | 1 | 2 | 3
Gastroenteritis | 1 | 3 | 3 | 2
Hearing and Vestibular Disorders
Tinnitus | 1 | <1 | 1 | 2
Metabolic and Nutritional Disorders
Weight decrease | 1 | 6 | 9 | 11
Thirst | <1 | 2 | 2 | 1
Musculoskeletal System Disorders
Arthralgia | 2 | 7 | 3 | 1
Neoplasms
Neoplasm | <1 | 2 | <1 | <1
Psychiatric Disorders
Anorexia | 6 | 9 | 15 | 14
Somnolence | 5 | 8 | 7 | 10
Difficulty with memory | 2 | 7 | 7 | 11
Difficulty with concentration/attention | 2 | 3 | 6 | 10
Insomnia | 5 | 6 | 7 | 6
Anxiety | 3 | 4 | 5 | 6
Mood problems | 2 | 3 | 6 | 5
Depression | 4 | 3 | 4 | 6
Nervousness | 2 | 4 | 4 | 4
Confusion | 2 | 2 | 3 | 4
Psychomotor slowing | 1 | 3 | 2 | 4
Libido decreased | 1 | 1 | 1 | 2
Aggravated depression | 1 | 1 | 2 | 2
Agitation | 1 | 2 | 2 | 1
Cognitive problems | 1 | <1 | 2 | 2
Reproductive Disorders, Female
Menstrual disorder | 2 | 3 | 2 | 2
Reproductive Disorders, Male
Ejaculation premature | 0 | 3 | 0 | 0
Resistance Mechanism Disorders
Viral infection | 3 | 4 | 4 | 3
Otitis media | <1 | 2 | 1 | 1
Respiratory System Disorders
Upper respiratory tract infection | 12 | 13 | 14 | 12
Sinusitis | 6 | 10 | 6 | 8
Pharyngitis | 4 | 5 | 6 | 2
Coughing | 2 | 2 | 4 | 3
Bronchitis | 2 | 3 | 3 | 3
Dyspnea | 2 | 1 | 3 | 2
Rhinitis | 1 | 1 | 2 | 2
Skin and Appendages Disorders
Pruritis | 2 | 4 | 2 | 2
Special Sense Other, Disorders
Taste perversion | 1 | 15 | 8 | 12
Taste loss | <1 | 1 | 1 | 2
Urinary System Disorders
Urinary tract infection | 2 | 4 | 2 | 4
Renal calculus | 0 | 0 | 1 | 2
Vision Disorders
Vision abnormal | <1 | 1 | 2 | 3
Blurred vision | 2 | 4 | 2 | 4
Conjunctivitis | 1 | 1 | 2 | 1

Of the 1135 patients exposed to TOPAMAX® in the placebo-controlled studies, 25% discontinued due to adverse reactions, compared to 10% of the 445 placebo patients. The adverse reactions associated with discontinuing therapy in the TOPAMAX® -treated patients included paresthesia (7%), fatigue (4%), nausea (4%), difficulty with concentration/attention (3%), insomnia (3%), anorexia (2%), and dizziness (2%).

Patients treated with TOPAMAX® experienced mean percent reductions in body weight that were dose-dependent. This change was not seen in the placebo group. Mean changes of 0%, -2%, -3%, and -4% were seen for the placebo group, TOPAMAX® 50, 100, and 200 mg groups, respectively.

Table 11 shows adverse reactions that were dose-dependent. Several central nervous system adverse reactions, including some that represented cognitive dysfunction, were dose-related. The most common dose-related adverse reactions were paresthesia, fatigue, nausea, anorexia, dizziness, difficulty with memory, diarrhea, weight decrease, difficulty with concentration/attention, and somnolence.

Table 11: Incidence (%) of Dose-Related Adverse Reactions From Placebo-Controlled, Migraine Trials [The incidence of adverse reactions in the 200 mg/day group was ≥ 2% than the incidence in both the placebo group and the 50 mg/day group.]
 |  | TOPAMAX® Dosage (mg/day)
 | Placebo | 50 | 100 | 200
Adverse Reaction | (N=445) | (N=235) | (N=386) | (N=514)
Paresthesia | 6 | 35 | 51 | 49
Fatigue | 11 | 14 | 15 | 19
Nausea | 8 | 9 | 13 | 14
Anorexia | 6 | 9 | 15 | 14
Dizziness | 10 | 8 | 9 | 12
Weight decrease | 1 | 6 | 9 | 11
Difficulty with memory | 2 | 7 | 7 | 11
Diarrhea | 4 | 9 | 11 | 11
Difficulty with concentration/attention | 2 | 3 | 6 | 10
Somnolence | 5 | 8 | 7 | 10
Hypoesthesia | 2 | 6 | 7 | 8
Anxiety | 3 | 4 | 5 | 6
Depression | 4 | 3 | 4 | 6
Mood problems | 2 | 3 | 6 | 5
Dry mouth | 2 | 2 | 3 | 5
Confusion | 2 | 2 | 3 | 4
Involuntary muscle contractions | 1 | 2 | 2 | 4
Abnormal vision | <1 | 1 | 2 | 3
Renal calculus | 0 | 0 | 1 | 2

6.8 Other Adverse Reactions Observed During Migraine Clinical Trials

TOPAMAX®, for the treatment of prophylaxis of migraine headache, has been administered to 1367 patients in all clinical studies (includes double-blind and open-label extension). During these studies, all adverse reactions were recorded by the clinical investigators using terminology of their own choosing. To provide a meaningful estimate of the proportion of individuals having adverse reactions, similar types of reactions were grouped into a smaller number of standardized categories using modified WHOART dictionary terminology.

The following additional adverse reactions that were not described earlier were reported by greater than 1% of the 1367 TOPAMAX®-treated patients in the controlled clinical trials:

Body as a Whole: Pain, chest pain, allergic reaction.

Central & Peripheral Nervous System Disorders: Headache, vertigo, tremor, sensory disturbance, migraine aggravated.

Gastrointestinal System Disorders: Constipation, gastroesophageal reflux.

Musculoskeletal System Disorders: Myalgia.

Platelet, Bleeding, and Clotting Disorders: Epistaxis.

Reproductive Disorders, Female: Intermenstrual bleeding.

Resistance Mechanism Disorders: Infection, genital moniliasis.

Respiratory System Disorders: Pneumonia, asthma.

Skin and Appendages Disorders: Rash, alopecia.

Vision Disorders: Abnormal accommodation, eye pain.

6.9 Postmarketing and Other Experience

In addition to the adverse experiences reported during clinical testing of TOPAMAX®, the following adverse experiences have been reported worldwide in patients receiving TOPAMAX® post-approval.

These adverse experiences have not been listed above and data are insufficient to support an estimate of their incidence or to establish causation. The listing is alphabetized: bullous skin reactions (including erythema multiforme, Stevens-Johnson syndrome, toxic epidermal necrolysis), hepatic failure (including fatalities), hepatitis, maculopathy, pancreatitis, and pemphigus.

7 DRUG INTERACTIONS

In vitro studies indicate that topiramate does not inhibit enzyme activity for CYP1A2, CYP2A6, CYP2B6, CYP2C9, CYP2D6, CYP2E1, and CYP3A4/5 isozymes. In vitro studies indicate that topiramate is a mild inhibitor of CYP2C19 and a mild inducer of CYP3A4. Drug interactions with some antiepileptic drugs, CNS depressants and oral contraceptives are described here. For other drug interactions, please refer to Clinical Pharmacology (12.3).

7.1 Antiepileptic Drugs

Potential interactions between topiramate and standard AEDs were assessed in controlled clinical pharmacokinetic studies in patients with epilepsy. Concomitant administration of phenytoin or carbamazepine with topiramate decreased plasma concentrations of topiramate by 48% and 40%, respectively when compared to TOPAMAX® given alone [see Clinical Pharmacology (12.3).]

Concomitant administration of valproic acid and TOPAMAX® has been associated with hyperammonemia with and without encephalopathy. Concomitant administration of TOPAMAX® with valproic acid has also been associated with hypothermia (with and without hyperammonemia) in patients who have tolerated either drug alone. It may be prudent to examine blood ammonia levels in patients in whom the onset of hypothermia has been reported [see Warnings and Precautions (5.9), (5.11) or Clinical Pharmacology (12.3)].

7.2 CNS Depressants

Concomitant administration of TOPAMAX® and alcohol or other CNS depressant drugs has not been evaluated in clinical studies. Because of the potential of topiramate to cause CNS depression, as well as other cognitive and/or neuropsychiatric adverse reactions, TOPAMAX® should be used with extreme caution if used in combination with alcohol and other CNS depressants.

7.3 Oral Contraceptives

Exposure to ethinyl estradiol was statistically significantly decreased at doses of 200, 400, and 800 mg/day (18%, 21%, and 30%, respectively) when TOPAMAX® was given as adjunctive therapy in patients taking valproic acid. However, norethindrone exposure was not significantly affected. In another pharmacokinetic interaction study in healthy volunteers with a concomitantly administered combination oral contraceptive product containing 1 mg norethindrone (NET) plus 35 mcg ethinyl estradiol (EE), TOPAMAX®, given in the absence of other medications at doses of 50 to 200 mg/day, was not associated with statistically significant changes in mean exposure (AUC) to either component of the oral contraceptive. The possibility of decreased contraceptive efficacy and increased breakthrough bleeding should be considered in patients taking combination oral contraceptive products with TOPAMAX®. Patients taking estrogen-containing contraceptives should be asked to report any change in their bleeding patterns. Contraceptive efficacy can be decreased even in the absence of breakthrough bleeding [see Clinical Pharmacology (12.3)].

7.4 Metformin

Topiramate treatment can frequently cause metabolic acidosis, a condition for which the use of metformin is contraindicated [see Clinical Pharmacology (12.3)].

7.5 Lithium

In patients, lithium levels were unaffected during treatment with topiramate at doses of 200 mg/day; however, there was an observed increase in systemic exposure of lithium (27% for Cmax and 26% for AUC) following topiramate doses of up to 600 mg/day. Lithium levels should be monitored when co-administered with high-dose TOPAMAX® [see Clinical Pharmacology (12.3)].

7.6 Other Carbonic Anhydrase Inhibitors

Concomitant use of topiramate, a carbonic anhydrase inhibitor, with any other carbonic anhydrase inhibitor (e.g., zonisamide, acetazolamide, or dichlorphenamide) may increase the severity of metabolic acidosis and may also increase the risk of kidney stone formation. Therefore, if TOPAMAX® is given concomitantly with another carbonic anhydrase inhibitor, the patient should be monitored for the appearance or worsening of metabolic acidosis [see Clinical Pharmacology (12.3)].

8 USE IN SPECIFIC POPULATIONS

8.1 Pregnancy

TERATOGENIC EFFECTS

Pregnancy Category D. [see Warnings and Precautions (5.6)]

TOPAMAX® (topiramate) can cause fetal harm when administered to a pregnant woman. Data from pregnancy registries indicate that infants exposed to topiramate in utero have an increased risk for cleft lip and/or cleft palate (oral clefts). When multiple species of pregnant animals received topiramate at clinically relevant doses, structural malformations, including craniofacial defects, and reduced fetal weights occurred in offspring. TOPAMAX® should be used during pregnancy only if the potential benefit outweighs the potential risk. If this drug is used during pregnancy, or if the patient becomes pregnant while taking this drug, the patient should be apprised of the potential hazard to a fetus [see Use in Specific Populations (8.9)].

Pregnancy Registry

Patients should be encouraged to enroll in the North American Antiepileptic Drug (NAAED) Pregnancy Registry if they become pregnant. This registry is collecting information about the safety of antiepileptic drugs during pregnancy. To enroll, patients can call the toll-free number 1-888-233-2334. Information about the North American Drug Pregnancy Registry can be found at http://www.massgeneral.org/aed/.

Human Data

Data from the NAAED Pregnancy Registry indicate an increased risk of oral clefts in infants exposed to topiramate monotherapy during the first trimester of pregnancy. The prevalence of oral clefts was 1.2% compared to a prevalence of 0.39% – 0.46% in infants exposed to other AEDs, and a prevalence of 0.12% in infants of mothers without epilepsy or treatment with other AEDs. For comparison, the Centers for Disease Control and Prevention (CDC) reviewed available data on oral clefts in the United States and found a similar background rate of 0.17%. The relative risk of oral clefts in topiramate-exposed pregnancies in the NAAED Pregnancy Registry was 9.6 (95% Confidence Interval = CI 3.6 – 25.7) as compared to the risk in a background population of untreated women. The UK Epilepsy and Pregnancy Register reported a similarly increased prevalence of oral clefts of 3.2% among infants exposed to topiramate monotherapy. The observed rate of oral clefts was 16 times higher than the background rate in the UK, which is approximately 0.2%.

TOPAMAX® treatment can cause metabolic acidosis [see Warnings and Precautions (5.3)]. The effect of topiramate-induced metabolic acidosis has not been studied in pregnancy; however, metabolic acidosis in pregnancy (due to other causes) can cause decreased fetal growth, decreased fetal oxygenation, and fetal death, and may affect the fetus' ability to tolerate labor. Pregnant patients should be monitored for metabolic acidosis and treated as in the nonpregnant state [see Warnings and Precautions (5.3)]. Newborns of mothers treated with TOPAMAX® should be monitored for metabolic acidosis because of transfer of topiramate to the fetus and possible occurrence of transient metabolic acidosis following birth.

Animal Data

Topiramate has demonstrated selective developmental toxicity, including teratogenicity, in multiple animal species at clinically relevant doses. When oral doses of 20, 100, or 500 mg/kg were administered to pregnant mice during the period of organogenesis, the incidence of fetal malformations (primarily craniofacial defects) was increased at all doses. The low dose is approximately 0.2 times the recommended human dose (RHD) 400 mg/day on a mg/m^2 basis. Fetal body weights and skeletal ossification were reduced at 500 mg/kg in conjunction with decreased maternal body weight gain.

In rat studies (oral doses of 20, 100, and 500 mg/kg or 0.2, 2.5, 30, and 400 mg/kg), the frequency of limb malformations (ectrodactyly, micromelia, and amelia) was increased among the offspring of dams treated with 400 mg/kg (10 times the RHD on a mg/m^2 basis) or greater during the organogenesis period of pregnancy. Embryotoxicity (reduced fetal body weights, increased incidence of structural variations) was observed at doses as low as 20 mg/kg (0.5 times the RHD on a mg/m^2 basis). Clinical signs of maternal toxicity were seen at 400 mg/kg and above, and maternal body weight gain was reduced during treatment with 100 mg/kg or greater.

In rabbit studies (20, 60, and 180 mg/kg or 10, 35, and 120 mg/kg orally during organogenesis), embryo/fetal mortality was increased at 35 mg/kg (2 times the RHD on a mg/m^2 basis) or greater, and teratogenic effects (primarily rib and vertebral malformations) were observed at 120 mg/kg (6 times the RHD on a mg/m^2 basis). Evidence of maternal toxicity (decreased body weight gain, clinical signs, and/or mortality) was seen at 35 mg/kg and above.

When female rats were treated during the latter part of gestation and throughout lactation (0.2, 4, 20, and 100 mg/kg or 2, 20, and 200 mg/kg), offspring exhibited decreased viability and delayed physical development at 200 mg/kg (5 times the RHD on a mg/m^2 basis) and reductions in pre- and/or postweaning body weight gain at 2 mg/kg (0.05 times the RHD on a mg/m^2 basis) and above. Maternal toxicity (decreased body weight gain, clinical signs) was evident at 100 mg/kg or greater.

In a rat embryo/fetal development study with a postnatal component (0.2, 2.5, 30, or 400 mg/kg during organogenesis; noted above), pups exhibited delayed physical development at 400 mg/kg (10 times the RHD on a mg/m^2 basis) and persistent reductions in body weight gain at 30 mg/kg (1 times the RHD on a mg/m^2 basis) and higher.

8.2 Labor and Delivery

Although the effect of TOPAMAX® on labor and delivery in humans has not been established, the development of topiramate-induced metabolic acidosis in the mother and/or in the fetus might affect the fetus' ability to tolerate labor [see Use in Specific Populations (8.1)].

8.3 Nursing Mothers

Limited data on 5 breastfeeding infants exposed to topiramate showed infant plasma topiramate levels equal to 10–20% of the maternal plasma level. The effects of this exposure on infants are unknown. Caution should be exercised when administered to a nursing woman.

8.4 Pediatric Use

Adjunctive Treatment for Partial Onset Epilepsy in Infants and Toddlers (1 to 24 months)

Safety and effectiveness in patients below the age of 2 years have not been established for the adjunctive therapy treatment of partial onset seizures, primary generalized tonic-clonic seizures, or seizures associated with Lennox-Gastaut syndrome. In a single randomized, double-blind, placebo-controlled investigational trial, the efficacy, safety, and tolerability of topiramate oral liquid and sprinkle formulations as an adjunct to concurrent antiepileptic drug therapy in infants 1 to 24 months of age with refractory partial onset seizures were assessed. After 20 days of double-blind treatment, topiramate (at fixed doses of 5, 15, and 25 mg/kg/day) did not demonstrate efficacy compared with placebo in controlling seizures.

In general, the adverse reaction profile in this population was similar to that of older pediatric patients, although results from the above controlled study and an open-label, long-term extension study in these infants/toddlers (1 to 24 months old) suggested some adverse reactions/toxicities (not previously observed in older pediatric patients and adults; i.e., growth/length retardation, certain clinical laboratory abnormalities, and other adverse reactions/toxicities that occurred with a greater frequency and/or greater severity than had been recognized previously from studies in older pediatric patients or adults for various indications.

These very young pediatric patients appeared to experience an increased risk for infections (any topiramate dose 12%, placebo 0%) and of respiratory disorders (any topiramate dose 40%, placebo 16%). The following adverse reactions were observed in at least 3% of patients on topiramate and were 3% to 7% more frequent than in patients on placebo: viral infection, bronchitis, pharyngitis, rhinitis, otitis media, upper respiratory infection, cough, and bronchospasm. A generally similar profile was observed in older children [see Adverse Reactions (6)].

Topiramate resulted in an increased incidence of patients with increased creatinine (any topiramate dose 5%, placebo 0%), BUN (any topiramate dose 3%, placebo 0%), and protein (any topiramate dose 34%, placebo 6%), and an increased incidence of decreased potassium (any topiramate dose 7%, placebo 0%). This increased frequency of abnormal values was not dose-related. Creatinine was the only analyte showing a noteworthy increased incidence (topiramate 25 mg/kg/day 5%, placebo 0%) of a markedly abnormal increase [see Warnings and Precautions (5.15)]. The significance of these findings is uncertain.

Topiramate treatment also produced a dose-related increase in the percentage of patients who had a shift from normal at baseline to high/increased (above the normal reference range) in total eosinophil count at the end of treatment. The incidence of these abnormal shifts was 6 % for placebo, 10% for 5 mg/kg/day, 9% for 15 mg/kg/day, 14% for 25 mg/kg/day, and 11% for any topiramate dose [see Warnings and Precautions (5.15)]. There was a mean dose-related increase in alkaline phosphatase. The significance of these findings is uncertain.

Topiramate produced a dose-related increased incidence of treatment-emergent hyperammonemia [see Warnings and Precautions (5.9)].

Treatment with topiramate for up to 1 year was associated with reductions in Z SCORES for length, weight, and head circumference [see Warnings and Precautions (5.3) and Adverse Reactions (6)].

In open-label, uncontrolled experience, increasing impairment of adaptive behavior was documented in behavioral testing over time in this population. There was a suggestion that this effect was dose-related. However, because of the absence of an appropriate control group, it is not known if this decrement in function was treatment-related or reflects the patient's underlying disease (e.g., patients who received higher doses may have more severe underlying disease) [see Warnings and Precautions (5.5)].

In this open-label, uncontrolled study, the mortality was 37 deaths/1000 patient years. It is not possible to know whether this mortality rate is related to topiramate treatment, because the background mortality rate for a similar, significantly refractory, young pediatric population (1–24 months) with partial epilepsy is not known.

Monotherapy Treatment in Partial Onset Epilepsy in Patients <2 Years Old

Safety and effectiveness in patients below the age of 2 years have not been established for the monotherapy treatment of epilepsy.

Migraine Prophylaxis in Pediatrics

Safety and effectiveness in pediatric patients have not been established for the prophylaxis treatment of migraine headache.

Topiramate treatment produced a dose-related increased shift in serum creatinine from normal at baseline to an increased value at the end of 4 months treatment in adolescent patients (ages 12–16 years) who were treated for migraine prophylaxis in a double-blind, placebo-controlled study. The incidence of these abnormal shifts was 4% for placebo, 4% for 50 mg, and 18% for 100 mg [see Warnings and Precautions (5.15)].

Juvenile Animal Studies

When topiramate (30, 90, or 300 mg/kg/day) was administered orally to rats during the juvenile period of development (postnatal days 12 to 50), bone growth plate thickness was reduced in males at the highest dose, which is approximately 5–8 times the maximum recommended pediatric dose (9 mg/kg/day) on a body surface area (mg/m^2) basis.

8.5 Geriatric Use

In clinical trials, 3% of patients were over 60. No age-related differences in effectiveness or adverse effects were evident. However, clinical studies of topiramate did not include sufficient numbers of subjects aged 65 and over to determine whether they respond differently than younger subjects. Dosage adjustment may be necessary for elderly with impaired renal function (creatinine clearance rate <70 mL/min/1.73 m^2) due to reduced clearance of topiramate [see Clinical Pharmacology (12.3) and Dosage and Administration (2.5)].

8.6 Race and Gender Effects

Evaluation of effectiveness and safety in clinical trials has shown no race- or gender-related effects.

8.7 Renal Impairment

The clearance of topiramate was reduced by 42% in moderately renally impaired (creatinine clearance 30 to 69 mL/min/1.73m^2) and by 54% in severely renally impaired subjects (creatinine clearance <30 mL/min/1.73m^2) compared to normal renal function subjects (creatinine clearance >70 mL/min/1.73m^2). One-half the usual starting and maintenance dose is recommended in patients with moderate or severe renal impairment [see Dosage and Administration (2.6) and Clinical Pharmacology (12.3)].

8.8 Patients Undergoing Hemodialysis

Topiramate is cleared by hemodialysis at a rate that is 4 to 6 times greater than in a normal individual. Accordingly, a prolonged period of dialysis may cause topiramate concentration to fall below that required to maintain an anti-seizure effect. To avoid rapid drops in topiramate plasma concentration during hemodialysis, a supplemental dose of TOPAMAX® may be required.

The actual adjustment should take into account the duration of dialysis period, the clearance rate of the dialysis system being used, and the effective renal clearance of topiramate in the patient being dialyzed [see Dosage and Administration (2.4) and Clinical Pharmacology (12.3)]

8.9 Women of Childbearing Potential

Data from pregnancy registries indicate that infants exposed to TOPAMAX® in utero have an increased risk for cleft lip and/or cleft palate (oral clefts) [see Warnings and Precautions (5.6) and Use in Specific Populations (8.1)]. Consider the benefits and the risks of TOPAMAX® when prescribing this drug to women of childbearing potential, particularly when TOPAMAX® is considered for a condition not usually associated with permanent injury or death. Because of the risk of oral clefts to the fetus, which occur in the first trimester of pregnancy before many women know they are pregnant, all women of childbearing potential should be apprised of the potential hazard to the fetus from exposure to TOPAMAX®. If the decision is made to use TOPAMAX®, women who are not planning a pregnancy should use effective contraception [see Drug Interactions (7.3)]. Women who are planning a pregnancy should be counseled regarding the relative risks and benefits of TOPAMAX® use during pregnancy, and alternative therapeutic options should be considered for these patients [see Patient Counseling Information (17.6)].

9 DRUG ABUSE AND DEPENDENCE

9.1 Controlled Substance

TOPAMAX® (topiramate) is not a controlled substance.

9.2 Abuse

The abuse and dependence potential of TOPAMAX® has not been evaluated in human studies.

9.3 Dependence

TOPAMAX® has not been systematically studied in animals or humans for its potential for tolerance or physical dependence.

10 OVERDOSAGE

Overdoses of TOPAMAX® have been reported. Signs and symptoms included convulsions, drowsiness, speech disturbance, blurred vision, diplopia, mentation impaired, lethargy, abnormal coordination, stupor, hypotension, abdominal pain, agitation, dizziness and depression. The clinical consequences were not severe in most cases, but deaths have been reported after poly-drug overdoses involving TOPAMAX®.

Topiramate overdose has resulted in severe metabolic acidosis [see Warnings and Precautions (5.3)].

A patient who ingested a dose between 96 and 110 g topiramate was admitted to a hospital with a coma lasting 20 to 24 hours followed by full recovery after 3 to 4 days.

In acute TOPAMAX® overdose, if the ingestion is recent, the stomach should be emptied immediately by lavage or by induction of emesis. Activated charcoal has been shown to adsorb topiramate in vitro. Treatment should be appropriately supportive. Hemodialysis is an effective means of removing topiramate from the body.

11 DESCRIPTION

Topiramate is a sulfamate-substituted monosaccharide. TOPAMAX® (topiramate) Tablets are available as 25 mg, 50 mg, 100 mg, and 200 mg round tablets for oral administration. TOPAMAX® (topiramate capsules) Sprinkle Capsules are available as 15 mg and 25 mg sprinkle capsules for oral administration as whole capsules or opened and sprinkled onto soft food.

Topiramate is a white crystalline powder with a bitter taste. Topiramate is most soluble in alkaline solutions containing sodium hydroxide or sodium phosphate and having a pH of 9 to 10. It is freely soluble in acetone, chloroform, dimethylsulfoxide, and ethanol. The solubility in water is 9.8 mg/mL. Its saturated solution has a pH of 6.3. Topiramate has the molecular formula C12H21NO8S and a molecular weight of 339.36. Topiramate is designated chemically as 2,3:4,5-Di-O-isopropylidene-β-D-fructopyranose sulfamate and has the following structural formula:

TOPAMAX® Tablets contain the following inactive ingredients: lactose monohydrate, pregelatinized starch, microcrystalline cellulose, sodium starch glycolate, magnesium stearate, purified water, carnauba wax, hypromellose, titanium dioxide, polyethylene glycol, synthetic iron oxide, and polysorbate 80.

TOPAMAX® Sprinkle Capsules contain topiramate-coated beads in a hard gelatin capsule. The inactive ingredients are sugar spheres (sucrose and starch), povidone, cellulose acetate, gelatin, sorbitan monolaurate, sodium lauryl sulfate, titanium dioxide, and black pharmaceutical ink.

12 CLINICAL PHARMACOLOGY

12.1 Mechanism of Action

The precise mechanisms by which topiramate exerts its anticonvulsant and migraine prophylaxis effects are unknown; however, preclinical studies have revealed four properties that may contribute to topiramate's efficacy for epilepsy and migraine prophylaxis. Electrophysiological and biochemical evidence suggests that topiramate, at pharmacologically relevant concentrations, blocks voltage-dependent sodium channels, augments the activity of the neurotransmitter gamma-aminobutyrate at some subtypes of the GABA-A receptor, antagonizes the AMPA/kainate subtype of the glutamate receptor, and inhibits the carbonic anhydrase enzyme, particularly isozymes II and IV.

12.2 Pharmacodynamics

Topiramate has anticonvulsant activity in rat and mouse maximal electroshock seizure (MES) tests. Topiramate is only weakly effective in blocking clonic seizures induced by the GABAA receptor antagonist, pentylenetetrazole. Topiramate is also effective in rodent models of epilepsy, which include tonic and absence-like seizures in the spontaneous epileptic rat (SER) and tonic and clonic seizures induced in rats by kindling of the amygdala or by global ischemia.

12.3 Pharmacokinetics

The sprinkle formulation is bioequivalent to the immediate-release tablet formulation and, therefore, may be substituted as a therapeutic equivalent.

Absorption of topiramate is rapid, with peak plasma concentrations occurring at approximately 2 hours following a 400 mg oral dose. The relative bioavailability of topiramate from the tablet formulation is about 80% compared to a solution. The bioavailability of topiramate is not affected by food.

The pharmacokinetics of topiramate are linear with dose proportional increases in plasma concentration over the dose range studied (200 to 800 mg/day). The mean plasma elimination half-life is 21 hours after single or multiple doses. Steady-state is thus reached in about 4 days in patients with normal renal function. Topiramate is 15% to 41% bound to human plasma proteins over the blood concentration range of 0.5 to 250 µg/mL. The fraction bound decreased as blood concentration increased.

Carbamazepine and phenytoin do not alter the binding of topiramate. Sodium valproate, at 500 µg/mL (a concentration 5 to 10 times higher than considered therapeutic for valproate) decreased the protein binding of topiramate from 23% to 13%. Topiramate does not influence the binding of sodium valproate.

Metabolism and Excretion

Topiramate is not extensively metabolized and is primarily eliminated unchanged in the urine (approximately 70% of an administered dose). Six metabolites have been identified in humans, none of which constitutes more than 5% of an administered dose. The metabolites are formed via hydroxylation, hydrolysis, and glucuronidation. There is evidence of renal tubular reabsorption of topiramate. In rats, given probenecid to inhibit tubular reabsorption, along with topiramate, a significant increase in renal clearance of topiramate was observed. This interaction has not been evaluated in humans. Overall, oral plasma clearance (CL/F) is approximately 20 to 30 mL/min in adults following oral administration.

Special Populations

Renal Impairment

The clearance of topiramate was reduced by 42% in moderately renally impaired (creatinine clearance 30 to 69 mL/min/1.73m^2) and by 54% in severely renally impaired subjects (creatinine clearance <30 mL/min/1.73m^2) compared to normal renal function subjects (creatinine clearance >70 mL/min/1.73m^2). Since topiramate is presumed to undergo significant tubular reabsorption, it is uncertain whether this experience can be generalized to all situations of renal impairment. It is conceivable that some forms of renal disease could differentially affect glomerular filtration rate and tubular reabsorption resulting in a clearance of topiramate not predicted by creatinine clearance. In general, however, use of one-half the usual starting and maintenance dose is recommended in patients with moderate or severe renal impairment [see Dosage and Administration (2.4) and (2.5) and Warnings and Precautions (5.13)].

Hemodialysis

Topiramate is cleared by hemodialysis. Using a high-efficiency, counterflow, single pass-dialysate hemodialysis procedure, topiramate dialysis clearance was 120 mL/min with blood flow through the dialyzer at 400 mL/min. This high clearance (compared to 20 to 30 mL/min total oral clearance in healthy adults) will remove a clinically significant amount of topiramate from the patient over the hemodialysis treatment period. Therefore, a supplemental dose may be required [see Dosage and Administration (2.6)].

Hepatic Impairment

In hepatically impaired subjects, the clearance of topiramate may be decreased; the mechanism underlying the decrease is not well understood [see Dosage and Administration (2.7)].

Age, Gender, and Race

The pharmacokinetics of topiramate in elderly subjects (65 to 85 years of age, N=16) were evaluated in a controlled clinical study. The elderly subject population had reduced renal function (creatinine clearance [-20%]) compared to young adults. Following a single oral 100 mg dose, maximum plasma concentration for elderly and young adults was achieved at approximately 1 to 2 hours. Reflecting the primary renal elimination of topiramate, topiramate plasma and renal clearance were reduced 21% and 19%, respectively, in elderly subjects, compared to young adults. Similarly, topiramate half-life was longer (13%) in the elderly. Reduced topiramate clearance resulted in slightly higher maximum plasma concentration (23%) and AUC (25%) in elderly subjects than observed in young adults. Topiramate clearance is decreased in the elderly only to the extent that renal function is reduced. As recommended for all patients, dosage adjustment may be indicated in the elderly patient when impaired renal function (creatinine clearance rate ≤70 mL/min/1.73 m^2) is evident. It may be useful to monitor renal function in the elderly patient [see Dosage and Administration (2.4) and Warnings and Precautions (5.13)].

Clearance of topiramate in adults was not affected by gender or race.

Pediatric Pharmacokinetics

Pharmacokinetics of topiramate were evaluated in patients aged 2 to <16 years. Patients received either no or a combination of other antiepileptic drugs. A population pharmacokinetic model was developed on the basis of pharmacokinetic data from relevant topiramate clinical studies. This dataset contained data from 1217 subjects including 258 pediatric patients aged 2 to <16 years (95 pediatric patients <10 years of age).

Pediatric patients on adjunctive treatment exhibited a higher oral clearance (L/h) of topiramate compared to patients on monotherapy, presumably because of increased clearance from concomitant enzyme-inducing antiepileptic drugs. In comparison, topiramate clearance per kg is greater in pediatric patients than in adults and in young pediatric patients (down to 2 years) than in older pediatric patients. Consequently, the plasma drug concentration for the same mg/kg/day dose would be lower in pediatric patients compared to adults and also in younger pediatric patients compared to older pediatric patients. Clearance was independent of dose.

As in adults, hepatic enzyme-inducing antiepileptic drugs decrease the steady state plasma concentrations of topiramate.

Drug-Drug Interactions

Antiepileptic Drugs

Potential interactions between topiramate and standard AEDs were assessed in controlled clinical pharmacokinetic studies in patients with epilepsy. The effects of these interactions on mean plasma AUCs are summarized in Table 12.

In Table 12, the second column (AED concentration) describes what happens to the concentration of the AED listed in the first column when topiramate is added. The third column (topiramate concentration) describes how the co-administration of a drug listed in the first column modifies the concentration of topiramate in experimental settings when TOPAMAX® was given alone.

Table 12: Summary of AED Interactions with TOPAMAX®
AED Co-administered | AED Concentration | Topiramate Concentration
Phenytoin | NC or 25% increase | 48% decrease
Carbamazepine (CBZ) | NC | 40% decrease
CBZ epoxide | NC | NE
Valproic acid | 11% decrease | 14% decrease
Phenobarbital | NC | NE
Primidone | NC | NE
Lamotrigine | NC at TPM doses up to 400 mg/day | 13% decrease
NC = Less than 10% change in plasma concentration.
AED = Antiepileptic drug.
NE = Not Evaluated.
TPM = Topiramate

In addition to the pharmacokinetic interaction described in the above table, concomitant administration of valproic acid and TOPAMAX® has been associated with hyperammonemia with and without encephalopathy and hypothermia [see Warnings and Precautions (5.9), (5.11) and Drug Interactions (7.1)].

CNS Depressants

Concomitant administration of TOPAMAX® and alcohol or other CNS depressant drugs has not been evaluated in clinical studies. Because of the potential of TOPAMAX® to cause CNS depression, as well as other cognitive and/or neuropsychiatric adverse reactions, TOPAMAX® should be used with extreme caution if used in combination with alcohol and other CNS depressants [see Drug Interactions (7.2)].

Oral Contraceptives

In a pharmacokinetic interaction study in healthy volunteers with a concomitantly administered combination oral contraceptive product containing 1 mg norethindrone (NET) plus 35 mcg ethinyl estradiol (EE), TOPAMAX®, given in the absence of other medications at doses of 50 to 200 mg/day, was not associated with statistically significant changes in mean exposure (AUC) to either component of the oral contraceptive. In another study, exposure to EE was statistically significantly decreased at doses of 200, 400, and 800 mg/day (18%, 21%, and 30%, respectively) when given as adjunctive therapy in patients taking valproic acid. In both studies, TOPAMAX® (50 mg/day to 800 mg/day) did not significantly affect exposure to NET. Although there was a dose-dependent decrease in EE exposure for doses between 200 and 800 mg/day, there was no significant dose-dependent change in EE exposure for doses of 50 to 200 mg/day. The clinical significance of the changes observed is not known. The possibility of decreased contraceptive efficacy and increased breakthrough bleeding should be considered in patients taking combination oral contraceptive products with TOPAMAX®. Patients taking estrogen-containing contraceptives should be asked to report any change in their bleeding patterns. Contraceptive efficacy can be decreased even in the absence of breakthrough bleeding [see Drug Interactions (7.3)].

Digoxin

In a single-dose study, serum digoxin AUC was decreased by 12% with concomitant TOPAMAX® administration. The clinical relevance of this observation has not been established.

Hydrochlorothiazide

A drug-drug interaction study conducted in healthy volunteers evaluated the steady-state pharmacokinetics of hydrochlorothiazide (HCTZ) (25 mg q24h) and topiramate (96 mg q12h) when administered alone and concomitantly. The results of this study indicate that topiramate Cmax increased by 27% and AUC increased by 29% when HCTZ was added to topiramate. The clinical significance of this change is unknown. The addition of HCTZ to topiramate therapy may require an adjustment of the topiramate dose. The steady-state pharmacokinetics of HCTZ were not significantly influenced by the concomitant administration of topiramate. Clinical laboratory results indicated decreases in serum potassium after topiramate or HCTZ administration, which were greater when HCTZ and topiramate were administered in combination.

Metformin

Topiramate treatment can frequently cause metabolic acidosis, a condition for which the use of metformin is contraindicated.

A drug-drug interaction study conducted in healthy volunteers evaluated the steady-state pharmacokinetics of metformin (500 mg every 12 hr) and topiramate in plasma when metformin was given alone and when metformin and topiramate (100 mg every 12 hr) were given simultaneously. The results of this study indicated that the mean metformin Cmax and AUC0–12h increased by 17% and 25%, respectively, when topiramate was added. Topiramate did not affect metformin tmax. The clinical significance of the effect of topiramate on metformin pharmacokinetics is not known. Oral plasma clearance of topiramate appears to be reduced when administered with metformin. The clinical significance of the effect of metformin on topiramate pharmacokinetics is unclear [see Drug Interactions (7.4)].

Pioglitazone

A drug-drug interaction study conducted in healthy volunteers evaluated the steady-state pharmacokinetics of topiramate and pioglitazone when administered alone and concomitantly. A 15% decrease in the AUCτ,ss of pioglitazone with no alteration in Cmax,ss was observed. This finding was not statistically significant. In addition, a 13% and 16% decrease in Cmax,ss and AUCτ,ss respectively, of the active hydroxy-metabolite was noted as well as a 60% decrease in Cmax,ss and AUCτ,ss of the active keto-metabolite. The clinical significance of these findings is not known. When TOPAMAX® is added to pioglitazone therapy or pioglitazone is added to TOPAMAX® therapy, careful attention should be given to the routine monitoring of patients for adequate control of their diabetic disease state.

Glyburide

A drug-drug interaction study conducted in patients with type 2 diabetes evaluated the steady-state pharmacokinetics of glyburide (5 mg/day) alone and concomitantly with topiramate (150 mg/day). There was a 22% decrease in Cmax and a 25% reduction in AUC24 for glyburide during topiramate administration. Systemic exposure (AUC) of the active metabolites, 4-trans-hydroxy-glyburide (M1) and 3-cis-hydroxyglyburide (M2), was also reduced by 13% and 15%, and Cmax was reduced by 18% and 25%, respectively. The steady-state pharmacokinetics of topiramate were unaffected by concomitant administration of glyburide.

Lithium

In patients, the pharmacokinetics of lithium were unaffected during treatment with topiramate at doses of 200 mg/day; however, there was an observed increase in systemic exposure of lithium (27% for Cmax and 26% for AUC) following topiramate doses up to 600 mg/day. Lithium levels should be monitored when co-administered with high-dose TOPAMAX® [see Drug Interactions (7.5)].

Haloperidol

The pharmacokinetics of a single dose of haloperidol (5 mg) were not affected following multiple dosing of topiramate (100 mg every 12 hr) in 13 healthy adults (6 males, 7 females).

Amitriptyline

There was a 12% increase in AUC and Cmax for amitriptyline (25 mg per day) in 18 normal subjects (9 males, 9 females) receiving 200 mg/day of topiramate. Some subjects may experience a large increase in amitriptyline concentration in the presence of topiramate and any adjustments in amitriptyline dose should be made according to the patient's clinical response and not on the basis of plasma levels.

Sumatriptan

Multiple dosing of topiramate (100 mg every 12 hrs) in 24 healthy volunteers (14 males, 10 females) did not affect the pharmacokinetics of single-dose sumatriptan either orally (100 mg) or subcutaneously (6 mg).

Risperidone

When administered concomitantly with topiramate at escalating doses of 100, 250, and 400 mg/day, there was a reduction in risperidone systemic exposure (16% and 33% for steady-state AUC at the 250 and 400 mg/day doses of topiramate). No alterations of 9-hydroxyrisperidone levels were observed. Co-administration of topiramate 400 mg/day with risperidone resulted in a 14% increase in Cmax and a 12% increase in AUC12 of topiramate. There were no clinically significant changes in the systemic exposure of risperidone plus 9-hydroxyrisperidone or of topiramate; therefore, this interaction is not likely to be of clinical significance.

Propranolol

Multiple dosing of topiramate (200 mg/day) in 34 healthy volunteers (17 males, 17 females) did not affect the pharmacokinetics of propranolol following daily 160 mg doses. Propranolol doses of 160 mg/day in 39 volunteers (27 males, 12 females) had no effect on the exposure to topiramate, at a dose of 200 mg/day of topiramate.

Dihydroergotamine

Multiple dosing of topiramate (200 mg/day) in 24 healthy volunteers (12 males, 12 females) did not affect the pharmacokinetics of a 1 mg subcutaneous dose of dihydroergotamine. Similarly, a 1 mg subcutaneous dose of dihydroergotamine did not affect the pharmacokinetics of a 200 mg/day dose of topiramate in the same study.

Diltiazem

Co-administration of diltiazem (240 mg Cardizem CD®) with topiramate (150 mg/day) resulted in a 10% decrease in Cmax and a 25% decrease in diltiazem AUC, a 27% decrease in Cmax and an 18% decrease in des-acetyl diltiazem AUC, and no effect on N-desmethyl diltiazem. Co-administration of topiramate with diltiazem resulted in a 16% increase in Cmax and a 19% increase in AUC12 of topiramate.

Venlafaxine

Multiple dosing of topiramate (150 mg/day) in healthy volunteers did not affect the pharmacokinetics of venlafaxine or O-desmethyl venlafaxine. Multiple dosing of venlafaxine (150 mg Effexor XR®) did not affect the pharmacokinetics of topiramate.

Other Carbonic Anhydrase Inhibitors

Concomitant use of topiramate, a carbonic anhydrase inhibitor, with any other carbonic anhydrase inhibitor (e.g., zonisamide, acetazolamide, or dichlorphenamide) may increase the severity of metabolic acidosis and may also increase the risk of kidney stone formation. Therefore, if TOPAMAX® is given concomitantly with another carbonic anhydrase inhibitor, the patient should be monitored for the appearance or worsening of metabolic acidosis [see Drug Interactions (7.6)].

Drug/Laboratory Tests Interactions

There are no known interactions of topiramate with commonly used laboratory tests.

13 NON-CLINICAL TOXICOLOGY

13.1 Carcinogenesis, Mutagenesis, and Impairment of Fertility

Carcinogenesis

An increase in urinary bladder tumors was observed in mice given topiramate (20, 75, and 300 mg/kg) in the diet for 21 months. The elevated bladder tumor incidence, which was statistically significant in males and females receiving 300 mg/kg, was primarily due to the increased occurrence of a smooth muscle tumor considered histomorphologically unique to mice. Plasma exposures in mice receiving 300 mg/kg were approximately 0.5 to 1 times steady-state exposures measured in patients receiving topiramate monotherapy at the recommended human dose (RHD) of 400 mg, and 1.5 to 2 times steady-state topiramate exposures in patients receiving 400 mg of topiramate plus phenytoin. The relevance of this finding to human carcinogenic risk is uncertain. No evidence of carcinogenicity was seen in rats following oral administration of topiramate for 2 years at doses up to 120 mg/kg (approximately 3 times the RHD on a mg/m^2 basis).

Mutagenesis

Topiramate did not demonstrate genotoxic potential when tested in a battery of in vitro and in vivo assays. Topiramate was not mutagenic in the Ames test or the in vitro mouse lymphoma assay; it did not increase unscheduled DNA synthesis in rat hepatocytes in vitro; and it did not increase chromosomal aberrations in human lymphocytes in vitro or in rat bone marrow in vivo.

Impairment of Fertility

No adverse effects on male or female fertility were observed in rats at doses up to 100 mg/kg (2.5 times the RHD on a mg/m^2 basis).

14 CLINICAL STUDIES

The studies described in the following sections were conducted using TOPAMAX® (topiramate) Tablets.

14.1 Monotherapy Epilepsy Controlled Trial

Patients with Partial Onset or Primary Generalized Tonic-Clonic Seizures

Adults and Pediatric Patients 10 Years of Age and Older

The effectiveness of topiramate as initial monotherapy in adults and children 10 years of age and older with partial onset or primary generalized tonic-clonic seizures was established in a multicenter, randomized, double-blind, parallel-group trial.

The trial was conducted in 487 patients diagnosed with epilepsy (6 to 83 years of age) who had 1 or 2 well-documented seizures during the 3-month retrospective baseline phase who then entered the study and received topiramate 25 mg/day for 7 days in an open-label fashion. Forty-nine percent of subjects had no prior AED treatment and 17% had a diagnosis of epilepsy for greater than 24 months. Any AED therapy used for temporary or emergency purposes was discontinued prior to randomization. In the double-blind phase, 470 patients were randomized to titrate up to 50 mg/day or 400 mg/day. If the target dose could not be achieved, patients were maintained on the maximum tolerated dose. Fifty-eight percent of patients achieved the maximal dose of 400 mg/day for >2 weeks, and patients who did not tolerate 150 mg/day were discontinued. The primary efficacy assessment was a between-group comparison of time to first seizure during the double-blind phase. Comparison of the Kaplan-Meier survival curves of time to first seizure favored the topiramate 400 mg/day group over the topiramate 50 mg/day group (p=0.0002, log rank test; Figure 1). The treatment effects with respect to time to first seizure were consistent across various patient subgroups defined by age, sex, geographic region, baseline body weight, baseline seizure type, time since diagnosis, and baseline AED use.

Figure 1: Kaplan-Meier Estimates of Cumulative Rates for Time to First Seizure

Children 2 to <10 Years of Age

The conclusion that topiramate is effective as initial monotherapy in children 2 to <10 years of age with partial onset or primary generalized tonic-clonic seizures was based on a pharmacometric bridging approach using data from the controlled epilepsy trials described in labeling. This approach consisted of first showing a similar exposure response relationship between pediatric patients down to 2 years of age and adults when topiramate was given as adjunctive therapy. Similarity of exposure-response was also demonstrated in pediatric patients ages 6 to <16 years and adults when topiramate was given as initial monotherapy. Specific dosing in children 2 to <10 years of age was derived from simulations utilizing plasma exposure ranges observed in pediatric and adult patients treated with topiramate initial monotherapy [see Dosage and Administration (2.1)].

14.2 Adjunctive Therapy Epilepsy Controlled Trials

Adult Patients With Partial Onset Seizures

The effectiveness of topiramate as an adjunctive treatment for adults with partial onset seizures was established in six multicenter, randomized, double-blind, placebo-controlled trials, two comparing several dosages of topiramate and placebo and four comparing a single dosage with placebo, in patients with a history of partial onset seizures, with or without secondarily generalized seizures.

Patients in these studies were permitted a maximum of two antiepileptic drugs (AEDs) in addition to TOPAMAX® tablets or placebo. In each study, patients were stabilized on optimum dosages of their concomitant AEDs during baseline phase lasting between 4 and 12 weeks. Patients who experienced a prespecified minimum number of partial onset seizures, with or without secondary generalization, during the baseline phase (12 seizures for 12-week baseline, 8 for 8-week baseline or 3 for 4-week baseline) were randomly assigned to placebo or a specified dose of TOPAMAX® tablets in addition to their other AEDs.

Following randomization, patients began the double-blind phase of treatment. In five of the six studies, patients received active drug beginning at 100 mg per day; the dose was then increased by 100 mg or 200 mg/day increments weekly or every other week until the assigned dose was reached, unless intolerance prevented increases. In the sixth study (119), the 25 or 50 mg/day initial doses of topiramate were followed by respective weekly increments of 25 or 50 mg/day until the target dose of 200 mg/day was reached. After titration, patients entered a 4, 8 or 12-week stabilization period. The numbers of patients randomized to each dose and the actual mean and median doses in the stabilization period are shown in Table 13.

Pediatric Patients Ages 2 to 16 Years with Partial Onset Seizures

The effectiveness of topiramate as an adjunctive treatment for pediatric patients ages 2 to 16 years with partial onset seizures was established in a multicenter, randomized, double-blind, placebo-controlled trial, comparing topiramate and placebo in patients with a history of partial onset seizures, with or without secondarily generalized seizures.

Patients in this study were permitted a maximum of two antiepileptic drugs (AEDs) in addition to TOPAMAX® tablets or placebo. In this study, patients were stabilized on optimum dosages of their concomitant AEDs during an 8-week baseline phase. Patients who experienced at least six partial onset seizures, with or without secondarily generalized seizures, during the baseline phase were randomly assigned to placebo or TOPAMAX® tablets in addition to their other AEDs.

Following randomization, patients began the double-blind phase of treatment. Patients received active drug beginning at 25 or 50 mg/day; the dose was then increased by 25 mg to 150 mg/day increments every other week until the assigned dosage of 125, 175, 225, or 400 mg/day based on patients' weight to approximate a dosage of 6 mg/kg/day was reached, unless intolerance prevented increases. After titration, patients entered an 8-week stabilization period.

Patients With Primary Generalized Tonic-Clonic Seizures

The effectiveness of topiramate as an adjunctive treatment for primary generalized tonic-clonic seizures in patients 2 years old and older was established in a multicenter, randomized, double-blind, placebo-controlled trial, comparing a single dosage of topiramate and placebo.

Patients in this study were permitted a maximum of two antiepileptic drugs (AEDs) in addition to TOPAMAX® or placebo. Patients were stabilized on optimum dosages of their concomitant AEDs during an 8-week baseline phase. Patients who experienced at least three primary generalized tonic-clonic seizures during the baseline phase were randomly assigned to placebo or TOPAMAX® in addition to their other AEDs.

Following randomization, patients began the double-blind phase of treatment. Patients received active drug beginning at 50 mg/day for four weeks; the dose was then increased by 50 mg to 150 mg/day increments every other week until the assigned dose of 175, 225, or 400 mg/day based on patients' body weight to approximate a dosage of 6 mg/kg/day was reached, unless intolerance prevented increases. After titration, patients entered a 12-week stabilization period.

Patients With Lennox-Gastaut Syndrome

The effectiveness of topiramate as an adjunctive treatment for seizures associated with Lennox-Gastaut syndrome was established in a multicenter, randomized, double-blind, placebo-controlled trial comparing a single dosage of topiramate with placebo in patients 2 years of age and older.

Patients in this study were permitted a maximum of two antiepileptic drugs (AEDs) in addition to TOPAMAX® or placebo. Patients who were experiencing at least 60 seizures per month before study entry were stabilized on optimum dosages of their concomitant AEDs during a 4-week baseline phase. Following baseline, patients were randomly assigned to placebo or TOPAMAX® in addition to their other AEDs. Active drug was titrated beginning at 1 mg/kg/day for a week; the dose was then increased to 3 mg/kg/day for one week, then to 6 mg/kg/day. After titration, patients entered an 8-week stabilization period. The primary measures of effectiveness were the percent reduction in drop attacks and a parental global rating of seizure severity.

Table 13: Topiramate Dose Summary During the Stabilization Periods of Each of Six Double-Blind, Placebo-Controlled, Add-On Trials in Adults with Partial Onset Seizures [Dose-response studies were not conducted for other indications or pediatric partial onset seizures.]
 |  |  | Target Topiramate Dosage (mg/day)
Protocol | Stabilization Dose | Placebo [Placebo dosages are given as the number of tablets. Placebo target dosages were as follows: Protocol Y1, 4 tablets/day; Protocols YD and Y2, 6 tablets/day; Protocols Y3 and 119, 8 tablets/day; Protocol YE, 10 tablets/day.] | 200 | 400 | 600 | 800 | 1,000
YD | N | 42 | 42 | 40 | 41 | -- | --
YD | Mean Dose | 5.9 | 200 | 390 | 556 | -- | --
YD | Median Dose | 6.0 | 200 | 400 | 600 | -- | --
YE | N | 44 | -- | -- | 40 | 45 | 40
YE | Mean Dose | 9.7 | -- | -- | 544 | 739 | 796
YE | Median Dose | 10.0 | -- | -- | 600 | 800 | 1,000
Y1 | N | 23 | -- | 19 | -- | -- | --
Y1 | Mean Dose | 3.8 | -- | 395 | -- | -- | --
Y1 | Median Dose | 4.0 | -- | 400 | -- | -- | --
Y2 | N | 30 | -- | -- | 28 | -- | --
Y2 | Mean Dose | 5.7 | -- | -- | 522 | -- | --
Y2 | Median Dose | 6.0 | -- | -- | 600 | -- | --
Y3 | N | 28 | -- | -- | -- | 25 | --
Y3 | Mean Dose | 7.9 | -- | -- | -- | 568 | --
Y3 | Median Dose | 8.0 | -- | -- | -- | 600 | --
119 | N | 90 | 157 | -- | -- | -- | --
 | Mean Dose | 8 | 200 | -- | -- | -- | --
 | Median Dose | 8 | 200 | -- | -- | -- | --

In all add-on trials, the reduction in seizure rate from baseline during the entire double-blind phase was measured. The median percent reductions in seizure rates and the responder rates (fraction of patients with at least a 50% reduction) by treatment group for each study are shown below in Table 14. As described above, a global improvement in seizure severity was also assessed in the Lennox-Gastaut trial.

Table 14: Efficacy Results in Double-Blind, Placebo-Controlled, Add-On Epilepsy Trials
 |  |  | Target Topiramate Dosage (mg/day)
Protocol Efficacy Results |  | Placebo | 200 | 400 | 600 | 800 | 1,000 | ≈6 mg/kg/day [For Protocols YP and YTC, protocol-specified target dosages (<9.3 mg/kg/day) were assigned based on subject's weight to approximate a dosage of 6 mg/kg per day; these dosages corresponded to mg/day dosages of 125, 175, 225, and 400 mg/day.]
Partial Onset Seizures
Studies in Adults
YD | N | 45 | 45 | 45 | 46 | -- | -- | --
Median % Reduction |  | 11.6 | 27.2 | 47.5 | 44.7 [p≤0.001;] | -- | -- | --
% Responders |  | 18 | 24 | 44 [p≤0.050;] | 46 | -- | -- | --
YE | N | 47 | -- | -- | 48 | 48 | 47 | --
Median % Reduction |  | 1.7 | -- | -- | 40.8 | 41.0 | 36.0 | --
% Responders |  | 9 | -- | -- | 40 | 41 | 36 | --
Y1 | N | 24 | -- | 23 | -- | -- | -- | --
Median % Reduction |  | 1.1 | -- | 40.7 | -- | -- | -- | --
% Responders |  | 8 | -- | 35 | -- | -- | -- | --
Y2 | N | 30 | -- | -- | 30 | -- | -- | --
Median % Reduction |  | -12.2 | -- | -- | 46.4 [p≤0.005;] | -- | -- | --
% Responders |  | 10 | -- | -- | 47 | -- | -- | --
Y3 | N | 28 | -- | -- | -- | 28 | -- | --
Median % Reduction |  | -20.6 | -- | -- | -- | 24.3 | -- | --
% Responders |  | 0 | -- | -- | -- | 43 | -- | --
119 N |  | 91 | 168 | -- | -- | -- | -- | --
Median % Reduction |  | 20.0 | 44.2 | -- | -- | -- | -- | --
% Responders |  | 24 | 45 | -- | -- | -- | -- | --
Studies in Pediatric Patients
YP | N | 45 | -- | -- | -- | -- | -- | 41
Median % Reduction |  | 10.5 | -- | -- | -- | -- | -- | 33.1
% Responders |  | 20 | -- | -- | -- | -- | -- | 39
Primary Generalized Tonic-Clonic [Median % reduction and % responders are reported for PGTC Seizures;]
YTC | N | 40 | -- | -- | -- | -- | -- | 39
Median % Reduction |  | 9.0 | -- | -- | -- | -- | -- | 56.7
% Responders |  | 20 | -- | -- | -- | -- | -- | 56
Lennox-Gastaut Syndrome [Median % reduction and % responders for drop attacks, i.e., tonic or atonic seizures;]
YL | N | 49 | -- | -- | -- | -- | -- | 46
Median % Reduction |  | -5.1 | -- | -- | -- | -- | -- | 14.8
% Responders |  | 14 | -- | -- | -- | -- | -- | 28 [p=0.071;]
Improvement in Seizure Severity [Percent of subjects who were minimally, much, or very much improved from baseline] |  | 28 | -- | -- | -- | -- | -- | 52
Comparisons with placebo:

Subset analyses of the antiepileptic efficacy of TOPAMAX® tablets in these studies showed no differences as a function of gender, race, age, baseline seizure rate, or concomitant AED.

In clinical trials for epilepsy, daily dosages were decreased in weekly intervals by 50 to 100 mg/day in adults and over a 2- to 8-week period in children; transition was permitted to a new antiepileptic regimen when clinically indicated.

14.3 Migraine Prophylaxis

The results of 2 multicenter, randomized, double-blind, placebo-controlled, parallel-group clinical trials established the effectiveness of TOPAMAX® in the prophylactic treatment of migraine headache. The design of both trials (one study was conducted in the U.S. and one study was conducted in the U.S. and Canada) was identical, enrolling patients with a history of migraine, with or without aura, for at least 6 months, according to the International Headache Society diagnostic criteria. Patients with a history of cluster headaches or basilar, ophthalmoplegic, hemiplegic, or transformed migraine headaches were excluded from the trials. Patients were required to have completed up to a 2-week washout of any prior migraine preventive medications before starting the baseline phase.

Patients who experienced 3 to 12 migraine headaches over the 4 weeks in the baseline phase were equally randomized to either TOPAMAX® 50 mg/day, 100 mg/day, 200 mg/day, or placebo and treated for a total of 26 weeks (8-week titration period and 18-week maintenance period). Treatment was initiated at 25 mg/day for one week, and then the daily dosage was increased by 25 mg increments each week until reaching the assigned target dose or maximum tolerated dose (administered twice daily).

Effectiveness of treatment was assessed by the reduction in migraine headache frequency, as measured by the change in 4-week migraine rate from the baseline phase to double-blind treatment period in each TOPAMAX® treatment group compared to placebo in the Intent-To-Treat (ITT) population.

In the first study, a total of 469 patients (416 females, 53 males), ranging in age from 13 to 70 years, were randomized and provided efficacy data. Two hundred sixty-five patients completed the entire 26-week double-blind phase. The median average daily dosages were 47.8 mg/day, 88.3 mg/day, and 132.1 mg/day in the target dose groups of TOPAMAX® 50, 100, and 200 mg/day, respectively.

The mean migraine headache frequency rate at baseline was approximately 5.5 migraine headaches/28 days and was similar across treatment groups. The change in the mean 4-week migraine headache frequency from baseline to the double-blind phase was -1.3, -2.1, and -2.2 in the TOPAMAX® 50, 100, and 200 mg/day groups, respectively, versus -0.8 in the placebo group (see Figure 2). The differences between the TOPAMAX® 100 and 200 mg/day groups versus placebo were statistically significant (p<0.001 for both comparisons).

In the second study, a total of 468 patients (406 females, 62 males), ranging in age from 12 to 65 years, were randomized and provided efficacy data. Two hundred fifty-five patients completed the entire 26-week double-blind phase. The median average daily dosages were 46.5 mg/day, 85.6 mg/day, and 150.2 mg/day in the target dose groups of TOPAMAX® 50, 100, and 200 mg/day, respectively.

The mean migraine headache frequency rate at baseline was approximately 5.5 migraine headaches/28 days and was similar across treatment groups. The change in the mean 4-week migraine headache period frequency from baseline to the double-blind phase was -1.4, -2.1, and -2.4 in the TOPAMAX® 50, 100, and 200 mg/day groups, respectively, versus -1.1 in the placebo group (see Figure 2). The differences between the TOPAMAX® 100 and 200 mg/day groups versus placebo were statistically significant (p=0.008 and p <0.001, respectively).

In both studies, there were no apparent differences in treatment effect within age or gender subgroups. Because most patients were Caucasian, there were insufficient numbers of patients from different races to make a meaningful comparison of race.

For patients withdrawing from TOPAMAX®, daily dosages were decreased in weekly intervals by 25 to 50 mg/day.

Figure 2: Reduction in 4-Week Migraine Headache Frequency
(Studies TOPMAT-MIGR-001 and TOPMAT-MIGR-002)

16 HOW SUPPLIED/STORAGE AND HANDLING

TOPAMAX® Tablets

TOPAMAX® (topiramate) Tablets are available as debossed, coated, round tablets in the following strengths and colors:

25 mg cream tablet (debossed "OMN" on one side; "25" on the other) and are available in

Bottles of 30 | NDC 54868-4672-1
Bottles of 60 | NDC 54868-4672-0
Bottles of 90 | NDC 54868-4672-3

50 mg light yellow tablet (debossed "OMN" on one side; "50" on the other) and are available in

Bottles of 30 | NDC 54868-5343-1
Bottles of 60 | NDC 54868-5343-0

100 mg yellow tablet (debossed "OMN" on one side; "100" on the other) and are available in

Bottles of 10 | NDC 54868-4674-0
Bottles of 30 | NDC 54868-4674-1
Bottles of 60 | NDC 54868-4674-2

200 mg salmon tablet (debossed "OMN" on one side; "200" on the other) and are available in

Bottles of 30 | NDC 54868-5190-1

Storage and Handling

TOPAMAX® Tablets should be stored in tightly-closed containers at controlled room temperature (59° to 86°F, 15° to 30°C). Protect from moisture.

TOPAMAX® Sprinkle Capsules should be stored in tightly-closed containers at or below 25°C (77°F). Protect from moisture.

17 PATIENT COUNSELING INFORMATION

Patients and their caregivers should be informed of the availability of a Medication Guide, and they should be instructed to read the Medication Guide prior to taking TOPAMAX®. Patients should be instructed to take TOPAMAX® only as prescribed. See FDA-approved Medication Guide.

17.1 Eye Disorders

Patients taking TOPAMAX® should be told to seek immediate medical attention if they experience blurred vision, visual disturbances, or periorbital pain [see Warnings and Precautions (5.1)].

17.2 Oligohydrosis and Hyperthermia

Patients, especially pediatric patients, treated with TOPAMAX® should be monitored closely for evidence of decreased sweating and increased body temperature, especially in hot weather. Patients should be counseled to contact their healthcare professionals immediately if they develop these symptoms [see Warnings and Precautions (5.2)].

17.3 Metabolic Acidosis

Patients should be warned about the potential significant risk for metabolic acidosis that may be asymptomatic and may be associated with adverse effects on kidneys (e.g., kidney stones, nephrocalcinosis), bones (e.g., osteoporosis, osteomalacia, and/or rickets in children), and growth (e.g., growth delay/retardation) in pediatric patients, and on the fetus [see Warnings and Precautions (5.3) and Use in Specific Populations (8.1)].

17.4 Suicidal Behavior and Ideation

Patients, their caregivers, and families should be counseled that AEDs, including TOPAMAX®, may increase the risk of suicidal thoughts and behavior and should be advised of the need to be alert for the emergence or worsening of the signs and symptoms of depression, any unusual changes in mood or behavior or the emergence of suicidal thoughts, or behavior or thoughts about self-harm. Behaviors of concern should be reported immediately to healthcare providers [see Warnings and Precautions (5.4)].

17.5 Interference with Cognitive and Motor Performance

Patients should be warned about the potential for somnolence, dizziness, confusion, difficulty concentrating, or visual effects and should be advised not to drive or operate machinery until they have gained sufficient experience on TOPAMAX® to gauge whether it adversely affects their mental performance, motor performance, and/or vision [see Warnings and Precautions (5.5)].

Even when taking TOPAMAX® or other anticonvulsants, some patients with epilepsy will continue to have unpredictable seizures. Therefore, all patients taking TOPAMAX® for epilepsy should be told to exercise appropriate caution when engaging in any activities where loss of consciousness could result in serious danger to themselves or those around them (including swimming, driving a car, climbing in high places, etc.). Some patients with refractory epilepsy will need to avoid such activities altogether. Physicians should discuss the appropriate level of caution with their patients, before patients with epilepsy engage in such activities.

17.6 Fetal Toxicity

Inform pregnant women and women of childbearing potential that use of TOPAMAX® during pregnancy can cause fetal harm, including an increased risk for cleft lip and/or cleft palate (oral clefts), which occur early in pregnancy before many women know they are pregnant. There may also be risks to the fetus from chronic metabolic acidosis with use of TOPAMAX® during pregnancy [see Warnings and Precautions (5.6) and Use in Specific Populations (8.1), (8.9)]. When appropriate, prescribers should counsel pregnant women and women of childbearing potential about alternative therapeutic options. This is particularly important when TOPAMAX® use is considered for a condition not usually associated with permanent injury or death.

Prescribers should advise women of childbearing potential who are not planning a pregnancy to use effective contraception while using TOPAMAX®, keeping in mind that there is a potential for decreased contraceptive efficacy when using estrogen-containing birth control with topiramate [see Drug Interactions (7.3)].

Encourage pregnant women using TOPAMAX®, to enroll in the North American Antiepileptic Drug (NAAED) Pregnancy Registry. The registry is collecting information about the safety of antiepileptic drugs during pregnancy. To enroll, patients can call the toll-free number, 1-888-233-2334. Information about the North American Drug Pregnancy Registry can be found at http://www.massgeneral.org/aed/ [see Use in Specific Populations (8.1)].

17.7 Hyperammonemia and Encephalopathy

Patients should be warned about the possible development of hyperammonemia with or without encephalopathy. Although hyperammonemia may be asymptomatic, clinical symptoms of hyperammonemic encephalopathy often include acute alterations in level of consciousness and/or cognitive function with lethargy or vomiting. This hyperammonemia and encephalopathy can develop with TOPAMAX® treatment alone or with TOPAMAX® treatment with concomitant valproic acid (VPA).

Patients should be instructed to contact their physician if they develop unexplained lethargy, vomiting, or changes in mental status [see Warnings and Precautions (5.9)].

17.8 Kidney Stones

Patients, particularly those with predisposing factors, should be instructed to maintain an adequate fluid intake in order to minimize the risk of kidney stone formation [see Warnings and Precautions (5.10)].

Manufactured by: Janssen Ortho, LLC, Gurabo, Puerto Rico 00778

Manufactured for: Janssen Pharmaceuticals, Inc. Titusville, NJ 08560

© Janssen Pharmaceuticals, Inc. 2009

Revised January 2012

Relabeling and Repackaging by:
Physicians Total Care, Inc.
Tulsa, Oklahoma 74146

MEDICATION GUIDE

TOPAMAX® (TOE-PA-MAX)
(topiramate)
Tablets and Sprinkle Capsules

Read this Medication Guide before you start taking TOPAMAX® and each time you get a refill. There may be new information. This information does not take the place of talking to your healthcare provider about your medical condition or treatment. If you have any questions about TOPAMAX®, talk to your healthcare provider or pharmacist.

What is the most important information I should know about TOPAMAX®?

TOPAMAX® may cause eye problems. Serious eye problems include:

- any sudden decrease in vision with or without eye pain and redness,
- a blockage of fluid in the eye causing increased pressure in the eye (secondary angle closure glaucoma).
- These eye problems can lead to permanent loss of vision if not treated. You should call your healthcare provider right away if you have any new eye symptoms.

TOPAMAX® may cause decreased sweating and increased body temperature (fever). People, especially children, should be watched for signs of decreased sweating and fever, especially in hot temperatures. Some people may need to be hospitalized for this condition. Call your healthcare provider right away if you have a fever or decreased sweating.

TOPAMAX® can increase the level of acid in your blood (metabolic acidosis). If left untreated, metabolic acidosis can cause brittle or soft bones (osteoporosis, osteomalacia, osteopenia), kidney stones, can slow the rate of growth in children, and may possibly harm your baby if you are pregnant. Metabolic acidosis can happen with or without symptoms.

Sometimes people with metabolic acidosis will:

- feel tired
- not feel hungry (loss of appetite)
- feel changes in heartbeat
- have trouble thinking clearly

Your healthcare provider should do a blood test to measure the level of acid in your blood before and during your treatment with TOPAMAX®. If you are pregnant, you should talk to your healthcare provider about whether you have metabolic acidosis.

Like other antiepileptic drugs, TOPAMAX® may cause suicidal thoughts or actions in a very small number of people, about 1 in 500.

Call a healthcare provider right away if you have any of these symptoms, especially if they are new, worse, or worry you:

- thoughts about suicide or dying
- attempts to commit suicide
- new or worse depression
- new or worse anxiety
- feeling agitated or restless
- panic attacks
- trouble sleeping (insomnia)
- new or worse irritability
- acting aggressive, being angry, or violent
- acting on dangerous impulses
- an extreme increase in activity and talking (mania)
- other unusual changes in behavior or mood

Do not stop TOPAMAX® without first talking to a healthcare provider.

- Stopping TOPAMAX® suddenly can cause serious problems.
- Suicidal thoughts or actions can be caused by things other than medicines. If you have suicidal thoughts or actions, your healthcare provider may check for other causes.

How can I watch for early symptoms of suicidal thoughts and actions?

- Pay attention to any changes, especially sudden changes, in mood, behaviors, thoughts, or feelings.
- Keep all follow-up visits with your healthcare provider as scheduled.
- Call your healthcare provider between visits as needed, especially if you are worried about symptoms.

TOPAMAX® can harm your unborn baby.

- If you take TOPAMAX® during pregnancy, your baby has a higher risk for birth defects called cleft lip and cleft palate. These defects can begin early in pregnancy, even before you know you are pregnant.
- Cleft lip and cleft palate may happen even in children born to women who are not taking any medicines and do not have other risk factors.
- There may be other medicines to treat your condition that have a lower chance of birth defects.
- All women of childbearing age should talk to their healthcare providers about using other possible treatments instead of TOPAMAX®. If the decision is made to use TOPAMAX®, you should use effective birth control (contraception) unless you are planning to become pregnant. You should talk to your doctor about the best kind of birth control to use while you are taking TOPAMAX®.
- Tell your healthcare provider right away if you become pregnant while taking TOPAMAX®. You and your healthcare provider should decide if you will continue to take TOPAMAX® while you are pregnant.
- Metabolic acidosis may have harmful effects on your baby. Talk to your healthcare provider if TOPAMAX® has caused metabolic acidosis during your pregnancy.
- Pregnancy Registry: If you become pregnant while taking TOPAMAX®, talk to your healthcare provider about registering with the North American Antiepileptic Drug Pregnancy Registry. You can enroll in this registry by calling 1-888-233-2334. The purpose of this registry is to collect information about the safety of antiepileptic drugs during pregnancy.

What is TOPAMAX®?

TOPAMAX® is a prescription medicine used:

- to treat certain types of seizures (partial onset seizures and primary generalized tonic-clonic seizures) in adults and children 2 years and older,
- with other medicines to treat certain types of seizures (partial onset seizures, primary generalized tonic-clonic seizures, and seizures associated with Lennox-Gastaut syndrome) in adults and children 2 years and older,
- to prevent migraine headaches in adults.

What should I tell my healthcare provider before taking TOPAMAX®?

Before taking TOPAMAX®, tell your healthcare provider about all your medical conditions, including if you:

- have or have had depression, mood problems, or suicidal thoughts or behavior
- have kidney problems, have kidney stones, or are getting kidney dialysis
- have a history of metabolic acidosis (too much acid in the blood)
- have liver problems
- have weak, brittle, or soft bones (osteomalacia, osteoporosis, osteopenia, or decreased bone density)
- have lung or breathing problems
- have eye problems, especially glaucoma
- have diarrhea
- have a growth problem
- are on a diet high in fat and low in carbohydrates, which is called a ketogenic diet
- are having surgery
- are pregnant or plan to become pregnant
- are breastfeeding. TOPAMAX® passes into breast milk. It is not known if the TOPAMAX® that passes into breast milk can harm your baby. Talk to your healthcare provider about the best way to feed your baby if you take TOPAMAX®.

Tell your healthcare provider about all the medicines you take, including prescription and non-prescription medicines, vitamins, and herbal supplements. TOPAMAX® and other medicines may affect each other causing side effects.

Especially tell your healthcare provider if you take:

- Valproic acid (such as DEPAKENE® or DEPAKOTE®)
- any medicines that impair or decrease your thinking, concentration, or muscle coordination
- birth control pills. TOPAMAX® may make your birth control pills less effective. Tell your healthcare provider if your menstrual bleeding changes while you are taking birth control pills and TOPAMAX®.

Ask your healthcare provider if you are not sure if your medicine is listed above.

Know the medicines you take. Keep a list of them to show your healthcare provider and pharmacist each time you get a new medicine. Do not start a new medicine without talking with your healthcare provider.

How should I take TOPAMAX®?

- Take TOPAMAX® exactly as prescribed.
- Your healthcare provider may change your dose. Do not change your dose without talking to your healthcare provider.
- TOPAMAX® Tablets should be swallowed whole. Do not chew the tablets. They may leave a bitter taste.
- TOPAMAX® Sprinkle Capsules may be swallowed whole or may be opened and sprinkled on a teaspoon of soft food. Drink fluids right after eating the food and medicine mixture to make sure it is all swallowed.
- Do not store any medicine and food mixture for later use.
- TOPAMAX® can be taken before, during, or after a meal. Drink plenty of fluids during the day. This may help prevent kidney stones while taking TOPAMAX®.
- If you take too much TOPAMAX®, call your healthcare provider or poison control center right away or go to the nearest emergency room.
- If you miss a single dose of TOPAMAX®, take it as soon as you can. However, if you are within 6 hours of taking your next scheduled dose, wait until then to take your usual dose of TOPAMAX®, and skip the missed dose. Do not double your dose. If you have missed more than one dose, you should call your healthcare provider for advice.
- Do not stop taking TOPAMAX® without talking to your healthcare provider. Stopping TOPAMAX® suddenly may cause serious problems. If you have epilepsy and you stop taking TOPAMAX® suddenly, you may have seizures that do not stop. Your healthcare provider will tell you how to stop taking TOPAMAX® slowly.
- Your healthcare provider may do blood tests while you take TOPAMAX®.

What should I avoid while taking TOPAMAX®?

- Do not drink alcohol while taking TOPAMAX®. TOPAMAX® and alcohol can affect each other causing side effects such as sleepiness and dizziness.
- Do not drive a car or operate heavy machinery until you know how TOPAMAX® affects you. TOPAMAX® can slow your thinking and motor skills, and may affect vision.

What are the possible side effects of TOPAMAX®?

TOPAMAX® may cause serious side effects including:

See "What is the most important information I should know about TOPAMAX®?"

- Metabolic acidosis. Metabolic acidosis can cause:
  - tiredness
  - loss of appetite
  - irregular heartbeat
  - impaired consciousness
- High blood ammonia levels. High ammonia in the blood can affect your mental activities, slow your alertness, make you feel tired, or cause vomiting. This has happened when TOPAMAX® is taken with a medicine called valproic acid (DEPAKENE® and DEPAKOTE®).
- Low body temperature. Taking TOPAMAX® when you are also taking valproic acid can cause a drop in body temperature to less than 95°F, feeling tired, confusion, or coma.
- Kidney stones. Drink plenty of fluids when taking TOPAMAX® to decrease your chances of getting kidney stones.
- Effects on thinking and alertness. TOPAMAX® may affect how you think and cause confusion, problems with concentration, attention, memory, or speech. TOPAMAX® may cause depression or mood problems, tiredness, and sleepiness.
- Dizziness or loss of muscle coordination.

Call your healthcare provider right away if you have any of the symptoms above.

The most common side effects of TOPAMAX® include:

- tingling of the arms and legs (paresthesia)
- not feeling hungry
- nausea
- a change in the way foods taste
- diarrhea
- weight loss
- nervousness
- upper respiratory tract infection

Tell your healthcare provider about any side effect that bothers you or that does not go away.

These are not all the possible side effects of TOPAMAX®. For more information, ask your healthcare provider or pharmacist.

Call your doctor for medical advice about side effects. You may report side effects to FDA at 1-800-FDA-1088.

You may also report side effects to Janssen Pharmaceuticals, Inc. at 1-800-JANSSEN (1-800-526-7736).

How should I store TOPAMAX®?

- Store TOPAMAX® Tablets at room temperature, 59°F to 86°F (15°C to 30°C).
- Store TOPAMAX® Sprinkle Capsules at or below 77°F (25°C).
- Keep TOPAMAX® in a tightly closed container.
- Keep TOPAMAX® dry and away from moisture.
- Keep TOPAMAX® and all medicines out of the reach of children.

General information about TOPAMAX®.

Medicines are sometimes prescribed for purposes other than those listed in a Medication Guide. Do not use TOPAMAX® for a condition for which it was not prescribed. Do not give TOPAMAX® to other people, even if they have the same symptoms that you have. It may harm them.

This Medication Guide summarizes the most important information about TOPAMAX®. If you would like more information, talk with your healthcare provider. You can ask your pharmacist or healthcare provider for information about TOPAMAX® that is written for health professionals.

For more information, go to www.topamax.com or call 1-800-JANSSEN (1-800-526-7736).

What are the ingredients in TOPAMAX®?

Active ingredient: topiramate

Inactive ingredients:

- Tablets - lactose monohydrate, pregelatinized starch, microcrystalline cellulose, sodium starch glycolate, magnesium stearate, purified water, carnauba wax, hypromellose, titanium dioxide, polyethylene glycol, synthetic iron oxide, and polysorbate 80.
- Sprinkle Capsules - sugar spheres (sucrose and starch), povidone, cellulose acetate, gelatin, sorbitan monolaurate, sodium lauryl sulfate, titanium dioxide, and black pharmaceutical ink.

Revised January 2012

This Medication Guide has been approved by the U.S. Food and Drug Administration.

Manufactured by: Janssen Ortho, LLC, Gurabo, Puerto Rico 00778

Manufactured for: Janssen Pharmaceuticals, Inc., Titusville, NJ 08560

© Janssen Pharmaceuticals, Inc. 2009

PRINCIPAL DISPLAY PANEL - 25 mg Tablet Bottle Label

TopAMAX®
(topiramate) Tablets

25 mg

Rx only

CAUTION: Verify
Prescription
Before Dispensing

ATTENTION PHARMACIST:
Dispense Accompanying
Medication Guide to Each
Patient

PRINCIPAL DISPLAY PANEL - 50 mg Tablet Bottle Label

TopAMAX®
(topiramate) Tablets

50 mg

CAUTION: Verify Prescription
Before Dispensing

ATTENTION PHARMACIST:
Dispense Accompanying
Medication Guide to Each
Patient

Rx only

PRINCIPAL DISPLAY PANEL - 100 mg Tablet Bottle Label

TopAMAX®
(topiramate) Tablets

100 mg

CAUTION: Verify Prescription
Before Dispensing

ATTENTION PHARMACIST:
Dispense Accompanying
Medication Guide to Each
Patient

Rx only

PRINCIPAL DISPLAY PANEL - 200 mg Tablet Bottle Label

TopAMAX®
(topiramate) Tablets

200 mg

CAUTION: Verify Prescription
Before Dispensing

ATTENTION PHARMACIST:
Dispense Accompanying
Medication Guide to Each
Patient

Rx only